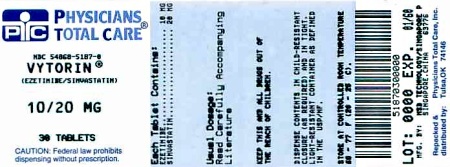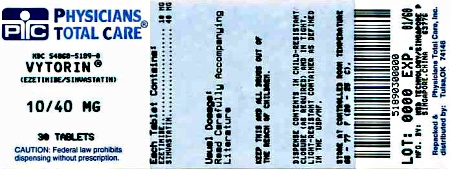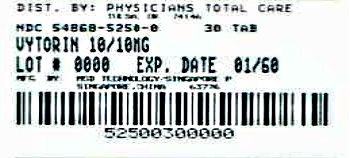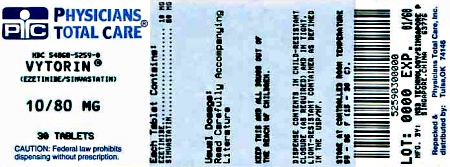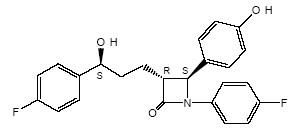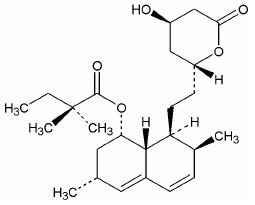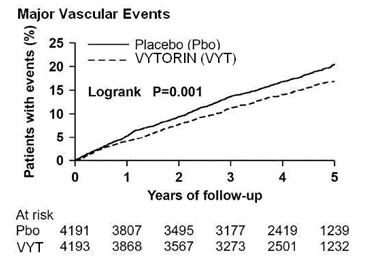 DRUG LABEL: VYTORIN
NDC: 54868-5250 | Form: TABLET
Manufacturer: Physicians Total Care, Inc.
Category: prescription | Type: HUMAN PRESCRIPTION DRUG LABEL
Date: 20120906

ACTIVE INGREDIENTS: ezetimibe 10 mg/1 1; simvastatin 10 mg/1 1
INACTIVE INGREDIENTS: butylated hydroxyanisole; citric acid monohydrate; croscarmellose sodium; HYPROMELLOSES; lactose monohydrate; magnesium stearate; propyl gallate; CELLULOSE, MICROCRYSTALLINE

HIGHLIGHTS OF PRESCRIBING INFORMATION

These highlights do not include all the information needed to use VYTORIN safely and effectively. See full prescribing information for VYTORIN.
VYTORIN® (ezetimibe/simvastatin) Tablets
Initial U.S. Approval: 2004

RECENT MAJOR CHANGES

Dosage and Administration

Recommended Dosing (2.1) 01/2012

Restricted Dosing for 10/80 mg (2.2) 06/2011

Coadministration with Other Drugs (2.3) 10/2011

Patients with Homozygous Familial Hypercholesterolemia (2.4) 06/2011

Patients with Renal Impairment/Chronic Kidney Disease (2.6) 01/2012

Chinese Patients Taking Lipid-Modifying Doses (≥1 g/day Niacin) of
Niacin-Containing Products (2.8) 06/2011

Contraindications (4) 02/2012

Warnings and Precautions

Myopathy/Rhabdomyolysis (5.1) 02/2012

Liver Enzymes (5.2) 01/2012

Endocrine Function (5.4) 10/2011

1 INDICATIONS AND USAGE

VYTORIN, which contains a cholesterol absorption inhibitor and an HMG-CoA reductase inhibitor (statin), is indicated as adjunctive therapy to diet to:

- reduce elevated total-C, LDL-C, Apo B, TG, and non-HDL-C, and to increase HDL-C in patients with primary (heterozygous familial and non-familial) hyperlipidemia or mixed hyperlipidemia. (1.1)
- reduce elevated total-C and LDL-C in patients with homozygous familial hypercholesterolemia (HoFH), as an adjunct to other lipid-lowering treatments. (1.2)

Limitations of Use (1.3)

- No incremental benefit of VYTORIN on cardiovascular morbidity and mortality over and above that demonstrated for simvastatin has been established.
- VYTORIN has not been studied in Fredrickson Type I, III, IV, and V dyslipidemias.

2 DOSAGE AND ADMINISTRATION

- Dose range is 10/10 mg/day to 10/40 mg/day. (2.1)
- Recommended usual starting dose is 10/10 or 10/20 mg/day. (2.1)
- Due to the increased risk of myopathy, including rhabdomyolysis, use of the 10/80-mg dose of VYTORIN should be restricted to patients who have been taking VYTORIN 10/80 mg chronically (e.g., for 12 months or more) without evidence of muscle toxicity. (2.2)
- Patients who are currently tolerating the 10/80-mg dose of VYTORIN who need to be initiated on an interacting drug that is contraindicated or is associated with a dose cap for simvastatin should be switched to an alternative statin or statin-based regimen with less potential for the drug-drug interaction. (2.2)
- Due to the increased risk of myopathy, including rhabdomyolysis, associated with the 10/80-mg dose of VYTORIN, patients unable to achieve their LDL-C goal utilizing the 10/40-mg dose of VYTORIN should not be titrated to the 10/80-mg dose, but should be placed on alternative LDL-C-lowering treatment(s) that provides greater LDL-C lowering. (2.2)
- Dosing of VYTORIN should occur either ≥2 hours before or ≥4 hours after administration of a bile acid sequestrant. (2.3, 7.5)

3 DOSAGE FORMS AND STRENGTHS

- Tablets (ezetimibe mg/simvastatin mg): 10/10, 10/20, 10/40, 10/80 (3)

4 CONTRAINDICATIONS

- Concomitant administration of strong CYP3A4 inhibitors. (4, 5.1)
- Concomitant administration of gemfibrozil, cyclosporine, or danazol. (4, 5.1)
- Hypersensitivity to any component of this medication (4, 6.2)
- Active liver disease or unexplained persistent elevations of hepatic transaminase levels (4, 5.2)
- Women who are pregnant or may become pregnant (4, 8.1)
- Nursing mothers (4, 8.3)

5 WARNINGS AND PRECAUTIONS

- Patients should be advised of the increased risk of myopathy, including rhabdomyolysis, with the 10/80-mg dose. (5.1)
- Patients should be advised to report promptly any symptoms of myopathy. VYTORIN should be discontinued immediately if myopathy is diagnosed or suspected. (5.1)
- Skeletal muscle effects (e.g., myopathy and rhabdomyolysis): Risks increase with higher doses and concomitant use of certain medicines. Predisposing factors include advanced age (≥65), female gender, uncontrolled hypothyroidism, and renal impairment. (4, 5.1, 8.5, 8.6)
- Liver enzyme abnormalities: Persistent elevations in hepatic transaminases can occur. Check liver enzyme tests before initiating therapy and as clinically indicated thereafter. (5.2)
- VYTORIN is not recommended in patients with moderate or severe hepatic impairment. (5.3, 12.3)

6 ADVERSE REACTIONS

- Common (incidence ≥2% and greater than placebo) adverse reactions in clinical trials: headache, increased ALT, myalgia, upper respiratory tract infection, and diarrhea. (6.1)

To report SUSPECTED ADVERSE REACTIONS, contact MSP Distribution Services (C) LLC, a subsidiary of Merck & Co., Inc., at 1-877-888-4231 or FDA at 1-800-FDA-1088 or www.fda.gov/medwatch.

7 DRUG INTERACTIONS

Drug Interactions Associated with Increased Risk of Myopathy/Rhabdomyolysis (2.3, 4, 5.1, 7.1, 7.2, 7.3, 7.6, 7.8, 12.3)
Interacting Agents | Prescribing Recommendations
Strong CYP3A4 Inhibitors, (e.g., itraconazole, ketoconazole, posaconazole, erythromycin, clarithromycin, telithromycin, HIV protease inhibitors, boceprevir, telaprevir, nefazodone), gemfibrozil, cyclosporine, danazol | Contraindicated with VYTORIN
Verapamil, diltiazem | Do not exceed 10/10 mg VYTORIN daily
Amiodarone, amlodipine, ranolazine | Do not exceed 10/20 mg VYTORIN daily
Grapefruit juice | Avoid large quantities of grapefruit juice (>1 quart daily)

- Coumarin anticoagulants: simvastatin prolongs INR. Achieve stable INR prior to starting VYTORIN. Monitor INR frequently until stable upon initiation or alteration of VYTORIN therapy. (7.8)
- Cholestyramine: Combination decreases exposure of ezetimibe. (2.3, 7.5)
- Other Lipid-lowering Medications: Use with other fibrate products or lipid-modifying doses (≥1 g/day) of niacin increases the risk of adverse skeletal muscle effects. Caution should be used when prescribing with VYTORIN. (5.1, 7.2, 7.4).

8 USE IN SPECIFIC POPULATIONS

- Moderate to severe renal impairment: Doses exceeding 10/20 mg/day should be used with caution and close monitoring (2.6, 8.6).

FULL PRESCRIBING INFORMATION

1 INDICATIONS AND USAGE

Therapy with lipid-altering agents should be only one component of multiple risk factor intervention in individuals at significantly increased risk for atherosclerotic vascular disease due to hypercholesterolemia. Drug therapy is indicated as an adjunct to diet when the response to a diet restricted in saturated fat and cholesterol and other nonpharmacologic measures alone has been inadequate.

1.1 Primary Hyperlipidemia

VYTORIN® is indicated for the reduction of elevated total cholesterol (total-C), low-density lipoprotein cholesterol (LDL-C), apolipoprotein B (Apo B), triglycerides (TG), and non-high-density lipoprotein cholesterol (non-HDL-C), and to increase high-density lipoprotein cholesterol (HDL-C) in patients with primary (heterozygous familial and non-familial) hyperlipidemia or mixed hyperlipidemia.

1.2 Homozygous Familial Hypercholesterolemia (HoFH)

VYTORIN is indicated for the reduction of elevated total-C and LDL-C in patients with homozygous familial hypercholesterolemia, as an adjunct to other lipid-lowering treatments (e.g., LDL apheresis) or if such treatments are unavailable.

1.3 Limitations of Use

No incremental benefit of VYTORIN on cardiovascular morbidity and mortality over and above that demonstrated for simvastatin has been established.

VYTORIN has not been studied in Fredrickson type I, III, IV, and V dyslipidemias.

2 DOSAGE AND ADMINISTRATION

2.1 Recommended Dosing

The usual dosage range is 10/10 mg/day to 10/40 mg/day. The recommended usual starting dose is 10/10 mg/day or 10/20 mg/day. VYTORIN should be taken as a single daily dose in the evening, with or without food. Patients who require a larger reduction in LDL-C (greater than 55%) may be started at 10/40 mg/day in the absence of moderate to severe renal impairment (estimated glomerular filtration rate <60 mL/min/1.73 m^2). After initiation or titration of VYTORIN, lipid levels may be analyzed after 2 or more weeks and dosage adjusted, if needed.

2.2 Restricted Dosing for 10/80 mg

Due to the increased risk of myopathy, including rhabdomyolysis, particularly during the first year of treatment, use of the 10/80-mg dose of VYTORIN should be restricted to patients who have been taking VYTORIN 10/80 mg chronically (e.g., for 12 months or more) without evidence of muscle toxicity [see Warnings and Precautions (5.1)].

Patients who are currently tolerating the 10/80-mg dose of VYTORIN who need to be initiated on an interacting drug that is contraindicated or is associated with a dose cap for simvastatin should be switched to an alternative statin or statin-based regimen with less potential for the drug-drug interaction.

Due to the increased risk of myopathy, including rhabdomyolysis, associated with the 10/80-mg dose of VYTORIN, patients unable to achieve their LDL-C goal utilizing the 10/40-mg dose of VYTORIN should not be titrated to the 10/80-mg dose, but should be placed on alternative LDL-C-lowering treatment(s) that provides greater LDL-C lowering.

2.3 Coadministration with Other Drugs

Patients taking Verapamil or Diltiazem

- The dose of VYTORIN should not exceed 10/10 mg/day [see Warnings and Precautions (5.1), Drug Interactions (7.3), and Clinical Pharmacology (12.3)].

Patients taking Amiodarone, Amlodipine or Ranolazine

- The dose of VYTORIN should not exceed 10/20 mg/day [see Warnings and Precautions (5.1), Drug Interactions (7.3), and Clinical Pharmacology (12.3)].

Patients taking Bile Acid Sequestrants

- Dosing of VYTORIN should occur either ≥2 hours before or ≥4 hours after administration of a bile acid sequestrant [see Drug Interactions (7.5)].

2.4 Patients with Homozygous Familial Hypercholesterolemia

The recommended dosage for patients with homozygous familial hypercholesterolemia is VYTORIN 10/40 mg/day in the evening [see Dosage and Administration, Restricted Dosing for 10/80 mg (2.2)]. VYTORIN should be used as an adjunct to other lipid-lowering treatments (e.g., LDL apheresis) in these patients or if such treatments are unavailable.

2.5 Patients with Hepatic Impairment

No dosage adjustment is necessary in patients with mild hepatic impairment [see Warnings and Precautions (5.3)].

2.6 Patients with Renal Impairment/Chronic Kidney Disease

In patients with mild renal impairment (estimated GFR ≥60 mL/min/1.73 m^2), no dosage adjustment is necessary. In patients with chronic kidney disease and estimated glomerular filtration rate <60 mL/min/1.73 m^2, the dose of VYTORIN is 10/20 mg/day in the evening. In such patients, higher doses should be used with caution and close monitoring [see Warnings and Precautions (5.1); Clinical Pharmacology (12.3)].

2.7 Geriatric Patients

No dosage adjustment is necessary in geriatric patients [see Clinical Pharmacology (12.3)].

2.8 Chinese Patients Taking Lipid-Modifying Doses (≥1 g/day Niacin) of Niacin-Containing Products

Because of an increased risk for myopathy in Chinese patients taking simvastatin 40 mg coadministered with lipid-modifying doses (≥1 g/day niacin) of niacin-containing products, caution should be used when treating Chinese patients with VYTORIN doses exceeding 10/20 mg/day coadministered with lipid-modifying doses (≥1 g/day niacin) of niacin-containing products. Because the risk for myopathy is dose-related, Chinese patients should not receive VYTORIN 10/80 mg coadministered with lipid-modifying doses of niacin-containing products. The cause of the increased risk of myopathy is not known. It is also unknown if the risk for myopathy with coadministration of simvastatin with lipid-modifying doses of niacin-containing products observed in Chinese patients applies to other Asian patients. [See Warnings and Precautions (5.1).]

3 DOSAGE FORMS AND STRENGTHS

- VYTORIN® 10/10, (ezetimibe 10 mg/simvastatin 10 mg tablets) are white to off-white capsule-shaped tablets with code "311" on one side.
- VYTORIN® 10/20, (ezetimibe 10 mg/simvastatin 20 mg tablets) are white to off-white capsule-shaped tablets with code "312" on one side.
- VYTORIN® 10/40, (ezetimibe 10 mg/simvastatin 40 mg tablets) are white to off-white capsule-shaped tablets with code "313" on one side.
- VYTORIN® 10/80, (ezetimibe 10 mg/simvastatin 80 mg tablets) are white to off-white capsule-shaped tablets with code "315" on one side.

4 CONTRAINDICATIONS

VYTORIN is contraindicated in the following conditions:

- Concomitant administration of strong CYP3A4 inhibitors (e.g., itraconazole, ketoconazole, posaconazole, HIV protease inhibitors, boceprevir, telaprevir, erythromycin, clarithromycin, telithromycin and nefazodone) [see Warnings and Precautions (5.1)].
- Concomitant administration of gemfibrozil, cyclosporine, or danazol [see Warnings and Precautions (5.1)].
- Hypersensitivity to any component of this medication [see Adverse Reactions (6.2)].
- Active liver disease or unexplained persistent elevations in hepatic transaminase levels [see Warnings and Precautions (5.2)].
- Women who are pregnant or may become pregnant. Serum cholesterol and triglycerides increase during normal pregnancy, and cholesterol or cholesterol derivatives are essential for fetal development. Because HMG-CoA reductase inhibitors (statins), such as simvastatin, decrease cholesterol synthesis and possibly the synthesis of other biologically active substances derived from cholesterol, VYTORIN may cause fetal harm when administered to a pregnant woman. Atherosclerosis is a chronic process and the discontinuation of lipid-lowering drugs during pregnancy should have little impact on the outcome of long-term therapy of primary hypercholesterolemia. There are no adequate and well-controlled studies of VYTORIN use during pregnancy; however, in rare reports congenital anomalies were observed following intrauterine exposure to statins. In rat and rabbit animal reproduction studies, simvastatin revealed no evidence of teratogenicity. VYTORIN should be administered to women of childbearing age only when such patients are highly unlikely to conceive. If the patient becomes pregnant while taking this drug, VYTORIN should be discontinued immediately and the patient should be apprised of the potential hazard to the fetus [see Use in Specific Populations (8.1)].
- Nursing mothers. It is not known whether simvastatin is excreted into human milk; however, a small amount of another drug in this class does pass into breast milk. Because statins have the potential for serious adverse reactions in nursing infants, women who require VYTORIN treatment should not breast-feed their infants [see Use in Specific Populations (8.3)].

5 WARNINGS AND PRECAUTIONS

5.1 Myopathy/Rhabdomyolysis

Simvastatin occasionally causes myopathy manifested as muscle pain, tenderness or weakness with creatine kinase above ten times the upper limit of normal (ULN). Myopathy sometimes takes the form of rhabdomyolysis with or without acute renal failure secondary to myoglobinuria, and rare fatalities have occurred. The risk of myopathy is increased by high levels of statin activity in plasma. Predisposing factors for myopathy include advanced age (≥65 years), female gender, uncontrolled hypothyroidism, and renal impairment.

The risk of myopathy, including rhabdomyolysis, is dose related. In a clinical trial database in which 41,413 patients were treated with simvastatin, 24,747 (approximately 60%) of whom were enrolled in studies with a median follow-up of at least 4 years, the incidence of myopathy was approximately 0.03% and 0.08% at 20 and 40 mg/day, respectively. The incidence of myopathy with 80 mg (0.61%) was disproportionately higher than that observed at the lower doses. In these trials, patients were carefully monitored and some interacting medicinal products were excluded.

In a clinical trial in which 12,064 patients with a history of myocardial infarction were treated with simvastatin (mean follow-up 6.7 years), the incidence of myopathy (defined as unexplained muscle weakness or pain with a serum creatine kinase [CK] >10 times upper limit of normal [ULN]) in patients on 80 mg/day was approximately 0.9% compared with 0.02% for patients on 20 mg/day. The incidence of rhabdomyolysis (defined as myopathy with a CK >40 times ULN) in patients on 80 mg/day was approximately 0.4% compared with 0% for patients on 20 mg/day. The incidence of myopathy, including rhabdomyolysis, was highest during the first year and then notably decreased during the subsequent years of treatment. In this trial, patients were carefully monitored and some interacting medicinal products were excluded.

The risk of myopathy, including rhabdomyolysis, is greater in patients on simvastatin 80 mg compared with other statin therapies with similar or greater LDL-C-lowering efficacy and compared with lower doses of simvastatin. Therefore, the 10/80-mg dose of VYTORIN should be used only in patients who have been taking VYTORIN 10/80 mg chronically (e.g., for 12 months or more) without evidence of muscle toxicity [see Dosage and Administration, Restricted Dosing for 10/80 mg (2.2)]. If, however, a patient who is currently tolerating the 10/80-mg dose of VYTORIN needs to be initiated on an interacting drug that is contraindicated or is associated with a dose cap for simvastatin, that patient should be switched to an alternative statin or statin-based regimen with less potential for the drug-drug interaction. Patients should be advised of the increased risk of myopathy, including rhabdomyolysis, and to report promptly any unexplained muscle pain, tenderness or weakness. If symptoms occur, treatment should be discontinued immediately [see Warnings and Precautions (5.2)].

In the Study of Heart and Renal Protection (SHARP), 9270 patients with chronic kidney disease were allocated to receive VYTORIN 10/20 mg daily (n=4650) or placebo (n=4620). During a median follow-up period of 4.9 years, the incidence of myopathy (defined as unexplained muscle weakness or pain with a serum creatine kinase [CK] >10 times upper limit of normal [ULN]) was 0.2% for VYTORIN and 0.1% for placebo: the incidence of rhabdomyolysis (defined as myopathy with a CK > 40 times ULN) was 0.09% for VYTORIN and 0.02% for placebo.

In post-marketing experience with ezetimibe, cases of myopathy and rhabdomyolysis have been reported. Most patients who developed rhabdomyolysis were taking a statin prior to initiating ezetimibe. However, rhabdomyolysis has been reported very rarely with ezetimibe monotherapy and very rarely with the addition of ezetimibe to agents known to be associated with increased risk of rhabdomyolysis, such as fibrates.

All patients starting therapy with VYTORIN or whose dose of VYTORIN is being increased should be advised of the risk of myopathy, including rhabdomyolysis, and told to report promptly any unexplained muscle pain, tenderness or weakness. VYTORIN therapy should be discontinued immediately if myopathy is diagnosed or suspected. In most cases, muscle symptoms and CK increases resolved when simvastatin treatment was promptly discontinued. Periodic CK determinations may be considered in patients starting therapy with simvastatin or whose dose is being increased, but there is no assurance that such monitoring will prevent myopathy.

Many of the patients who have developed rhabdomyolysis on therapy with simvastatin have had complicated medical histories, including renal insufficiency usually as a consequence of long-standing diabetes mellitus. Such patients taking VYTORIN merit closer monitoring.

VYTORIN therapy should be discontinued if markedly elevated CPK levels occur or myopathy is diagnosed or suspected. VYTORIN therapy should also be temporarily withheld in any patient experiencing an acute or serious condition predisposing to the development of renal failure secondary to rhabdomyolysis, e.g., sepsis; hypotension; major surgery; trauma; severe metabolic, endocrine, or electrolyte disorders; or uncontrolled epilepsy.

Drug Interactions

The risk of myopathy and rhabdomyolysis is increased by high levels of statin activity in plasma. Simvastatin is metabolized by the cytochrome P450 isoform 3A4. Certain drugs that inhibit this metabolic pathway can raise the plasma levels of simvastatin and may increase the risk of myopathy. These include itraconazole, ketoconazole, and posaconazole, the macrolide antibiotics erythromycin and clarithromycin, and the ketolide antibiotic telithromycin, HIV protease inhibitors, boceprevir, telaprevir, the antidepressant nefazodone, or large quantities of grapefruit juice (>1 quart daily). Combination of these drugs with VYTORIN is contraindicated. If treatment with itraconazole, ketoconazole, posaconazole, erythromycin, clarithromycin or telithromycin is unavoidable, therapy with VYTORIN must be suspended during the course of treatment. [See Contraindications (4) and Drug Interactions (7).] In vitro studies have demonstrated a potential for voriconazole to inhibit the metabolism of simvastatin. Adjustment of the VYTORIN dose may be needed to reduce the risk of myopathy/rhabdomyolysis if voriconazole must be used concomitantly with VYTORIN. [See Drug Interactions (7.1).]

The combined use of VYTORIN with gemfibrozil, cyclosporine, or danazol is contraindicated [see Contraindications (4) and Drug Interactions (7.1 and 7.2)].

Caution should be used when prescribing other fibrates with VYTORIN, as these agents can cause myopathy when given alone and the risk is increased when they are co-administered [see Drug Interactions (7.2, 7.7)].

Cases of myopathy, including rhabdomyolysis, have been reported with simvastatin coadministered with colchicine, and caution should be exercised when prescribing VYTORIN with colchicine [see Drug Interactions (7.9)].

The benefits of the combined use of VYTORIN with the following drugs should be carefully weighed against the potential risks of combinations: other lipid-lowering drugs (other fibrates or ≥1 g/day of niacin), amiodarone, verapamil, diltiazem, amlodipine, or ranolazine [see Drug Interactions (7.3) and Table 6 in Clinical Pharmacology (12.3)].

Cases of myopathy, including rhabdomyolysis, have been observed with simvastatin coadministered with lipid-modifying doses (≥1 g/day niacin) of niacin-containing products. In an ongoing, double-blind, randomized cardiovascular outcomes trial, an independent safety monitoring committee identified that the incidence of myopathy is higher in Chinese compared with non-Chinese patients taking simvastatin 40 mg or ezetimibe/simvastatin 10/40 mg coadministered with lipid-modifying doses of a niacin-containing product. Caution should be used when treating Chinese patients with VYTORIN in doses exceeding 10/20 mg/day coadministered with lipid-modifying doses of niacin-containing products. Because the risk for myopathy is dose-related, Chinese patients should not receive VYTORIN 10/80 mg coadministered with lipid-modifying doses of niacin-containing products. It is unknown if the risk for myopathy with coadministration of simvastatin with lipid-modifying doses of niacin-containing products observed in Chinese patients applies to other Asian patients [see Drug Interactions (7.4)].

Prescribing recommendations for interacting agents are summarized in Table 1 [see also Dosage and Administration (2.3), Drug Interactions (7), and Clinical Pharmacology (12.3)].

Table 1: Drug Interactions Associated with Increased Risk of Myopathy/Rhabdomyolysis
Interacting Agents | Prescribing Recommendations
Strong CYP3A4 Inhibitors, e.g.: Itraconazole Ketoconazole Posaconazole Erythromycin Clarithromycin Telithromycin HIV protease inhibitors Boceprevir Telaprevir Nefazodone Gemfibrozil Cyclosporine Danazol | Contraindicated with VYTORIN
Verapamil Diltiazem | Do not exceed 10/10 mg VYTORIN daily
Amiodarone Amlodipine Ranolazine | Do not exceed 10/20 mg VYTORIN daily
Grapefruit juice | Avoid large quantities of grapefruit juice (>1 quart daily)

5.2 Liver Enzymes

In three placebo-controlled, 12-week trials, the incidence of consecutive elevations (≥3 X ULN) in serum transaminases was 1.7% overall for patients treated with VYTORIN and appeared to be dose-related with an incidence of 2.6% for patients treated with VYTORIN 10/80. In controlled long-term (48-week) extensions, which included both newly-treated and previously-treated patients, the incidence of consecutive elevations (≥3 X ULN) in serum transaminases was 1.8% overall and 3.6% for patients treated with VYTORIN 10/80. These elevations in transaminases were generally asymptomatic, not associated with cholestasis, and returned to baseline after discontinuation of therapy or with continued treatment.

In SHARP, 9270 patients with chronic kidney disease were allocated to receive VYTORIN 10/20 mg daily (n=4650), or placebo (n=4620). During a median follow-up period of 4.9 years, the incidence of consecutive elevations of transaminases (>3 × ULN) was 0.7% for VYTORIN and 0.6% for placebo.

It is recommended that liver function tests be performed before the initiation of treatment with VYTORIN, and thereafter when clinically indicated. There have been rare postmarketing reports of fatal and non-fatal hepatic failure in patients taking statins, including simvastatin. If serious liver injury with clinical symptoms and/or hyperbilirubinemia or jaundice occurs during treatment with VYTORIN, promptly interrupt therapy. If an alternate etiology is not found do not restart VYTORIN. Note that ALT may emanate from muscle, therefore ALT rising with CK may indicate myopathy [see Warnings and Precautions (5.1)].

VYTORIN should be used with caution in patients who consume substantial quantities of alcohol and/or have a past history of liver disease. Active liver diseases or unexplained persistent transaminase elevations are contraindications to the use of VYTORIN.

5.3 Hepatic Impairment

Due to the unknown effects of the increased exposure to ezetimibe in patients with moderate or severe hepatic impairment, VYTORIN is not recommended in these patients. [See Clinical Pharmacology (12.3).]

5.4 Endocrine Function

Increases in HbA1c and fasting serum glucose levels have been reported with HMG-CoA reductase inhibitors, including simvastatin.

6 ADVERSE REACTIONS

The following serious adverse reactions are discussed in greater detail in other sections of the label:

- Rhabdomyolysis and myopathy [see Warnings and Precautions (5.1)]
- Liver enzyme abnormalities [see Warnings and Precautions (5.2)]

6.1 Clinical Trials Experience

VYTORIN

Because clinical studies are conducted under widely varying conditions, adverse reaction rates observed in the clinical studies of a drug cannot be directly compared to rates in the clinical studies of another drug and may not reflect the rates observed in practice.

In the VYTORIN (ezetimibe/simvastatin) placebo-controlled clinical trials database of 1420 patients (age range 20-83 years, 52% women, 87% Caucasians, 3% Blacks, 5% Hispanics, 3% Asians) with a median treatment duration of 27 weeks, 5% of patients on VYTORIN and 2.2% of patients on placebo discontinued due to adverse reactions.

The most common adverse reactions in the group treated with VYTORIN that led to treatment discontinuation and occurred at a rate greater than placebo were:

- Increased ALT (0.9%)
- Myalgia (0.6%)
- Increased AST (0.4%)
- Back pain (0.4%)

The most commonly reported adverse reactions (incidence ≥2% and greater than placebo) in controlled clinical trials were: headache (5.8%), increased ALT (3.7%), myalgia (3.6%), upper respiratory tract infection (3.6%), and diarrhea (2.8%).

VYTORIN has been evaluated for safety in more than 10,189 patients in clinical trials.

Table 2 summarizes the frequency of clinical adverse reactions reported in ≥2% of patients treated with VYTORIN (n=1420) and at an incidence greater than placebo, regardless of causality assessment, from four placebo-controlled trials.

Table 2: Clinical Adverse Reactions Occurring in ≥2% of Patients Treated with VYTORIN and at an Incidence Greater than Placebo, Regardless of Causality
Body System/Organ Class Adverse Reaction | Placebo (%) n=371 | Ezetimibe 10 mg (%) n=302 | Simvastatin [All doses.] (%) n=1234 | VYTORIN (%) n=1420
Body as a whole – general disorders
Headache | 5.4 | 6.0 | 5.9 | 5.8
Gastrointestinal system disorders
Diarrhea | 2.2 | 5.0 | 3.7 | 2.8
Infections and infestations
Influenza | 0.8 | 1.0 | 1.9 | 2.3
Upper respiratory tract infection | 2.7 | 5.0 | 5.0 | 3.6
Musculoskeletal and connective tissue disorders
Myalgia | 2.4 | 2.3 | 2.6 | 3.6
Pain in extremity | 1.3 | 3.0 | 2.0 | 2.3

Study of Heart and Renal Protection

In SHARP, 9270 patients were allocated to VYTORIN 10/20 mg daily (n=4650) or placebo (n=4620) for a median follow-up period of 4.9 years. The proportion of patients who permanently discontinued study treatment as a result of either an adverse event or abnormal safety blood result was 10.4% vs. 9.8% among patients allocated to VYTORIN and placebo, respectively. Comparing those allocated to VYTORIN vs. placebo, the incidence of myopathy (defined as unexplained muscle weakness or pain with a serum CK >10 times ULN) was 0.2% vs. 0.1% and the incidence of rhabdomyolysis (defined as myopathy with a CK >40 times ULN) was 0.09% vs. 0.02%, respectively. Consecutive elevations of transaminases (>3 × ULN) occurred in 0.7% vs. 0.6%, respectively. Patients were asked about the occurrence of unexplained muscle pain or weakness at each study visit: 21.5% vs. 20.9% patients ever reported muscle symptoms in the VYTORIN and placebo groups, respectively. Cancer was diagnosed during the trial in 9.4% vs. 9.5% of patients assigned to VYTORIN and placebo, respectively.

Ezetimibe

Other adverse reactions reported with ezetimibe in placebo-controlled studies, regardless of causality assessment: Musculoskeletal system disorders: arthralgia; Infections and infestations: sinusitis; Body as a whole – general disorders: fatigue.

Simvastatin

In a clinical trial in which 12,064 patients with a history of myocardial infarction were treated with simvastatin (mean follow-up 6.7 years), the incidence of myopathy (defined as unexplained muscle weakness or pain with a serum creatine kinase [CK] >10 times upper limit of normal [ULN]) in patients on 80 mg/day was approximately 0.9% compared with 0.02% for patients on 20 mg/day. The incidence of rhabdomyolysis (defined as myopathy with a CK >40 times ULN) in patients on 80 mg/day was approximately 0.4% compared with 0% for patients on 20 mg/day. The incidence of myopathy, including rhabdomyolysis, was highest during the first year and then notably decreased during the subsequent years of treatment. In this trial, patients were carefully monitored and some interacting medicinal products were excluded.

Other adverse reactions reported with simvastatin in placebo-controlled clinical studies, regardless of causality assessment: Cardiac disorders: atrial fibrillation; Ear and labyrinth disorders: vertigo; Gastrointestinal disorders: abdominal pain, constipation, dyspepsia, flatulence, gastritis; Skin and subcutaneous tissue disorders: eczema, rash; Endocrine disorders: diabetes mellitus; Infections and infestations: bronchitis, sinusitis, urinary tract infections; Body as a whole – general disorders: asthenia, edema/swelling; Psychiatric disorders: insomnia.

Laboratory Tests

Marked persistent increases of hepatic serum transaminases have been noted [see Warnings and Precautions (5.2)]. Elevated alkaline phosphatase and γ-glutamyl transpeptidase have been reported. About 5% of patients taking simvastatin had elevations of CK levels of 3 or more times the normal value on one or more occasions. This was attributable to the noncardiac fraction of CK [see Warnings and Precautions (5.1)].

6.2 Post-Marketing Experience

Because the below reactions are reported voluntarily from a population of uncertain size, it is generally not possible to reliably estimate their frequency or establish a causal relationship to drug exposure.

The following adverse reactions have been reported in post-marketing experience for VYTORIN or ezetimibe or simvastatin: pruritus; alopecia; erythema multiforme; a variety of skin changes (e.g., nodules, discoloration, dryness of skin/mucous membranes, changes to hair/nails); dizziness; muscle cramps; myalgia; arthralgia; pancreatitis; paresthesia; peripheral neuropathy; vomiting; nausea; anemia; erectile dysfunction; interstitial lung disease; myopathy/rhabdomyolysis [see Warnings and Precautions (5.1)]; hepatitis/jaundice; fatal and non-fatal hepatic failure; depression; cholelithiasis; cholecystitis; thrombocytopenia; elevations in liver transaminases; elevated creatine phosphokinase.

Hypersensitivity reactions, including anaphylaxis, angioedema, rash, and urticaria have been reported.

In addition, an apparent hypersensitivity syndrome has been reported rarely that has included one or more of the following features: anaphylaxis, angioedema, lupus erythematous-like syndrome, polymyalgia rheumatica, dermatomyositis, vasculitis, purpura, thrombocytopenia, leukopenia, hemolytic anemia, positive ANA, ESR increase, eosinophilia, arthritis, arthralgia, urticaria, asthenia, photosensitivity, fever, chills, flushing, malaise, dyspnea, toxic epidermal necrolysis, erythema multiforme, including Stevens-Johnson syndrome.

There have been rare postmarketing reports of cognitive impairment (e.g., memory loss, forgetfulness, amnesia, memory impairment, confusion) associated with statin use. These cognitive issues have been reported for all statins. The reports are generally nonserious, and reversible upon statin discontinuation, with variable times to symptom onset (1 day to years) and symptom resolution (median of 3 weeks).

7 DRUG INTERACTIONS

[See Clinical Pharmacology (12.3).]

VYTORIN

7.1 Strong CYP3A4 Inhibitors, cyclosporine, or danazol

Strong CYP3A4 inhibitors: The risk of myopathy is increased by reducing the elimination of the simvastatin component of VYTORIN. Hence when VYTORIN is used with an inhibitor of CYP3A4 (e.g., as listed below), elevated plasma levels of HMG-CoA reductase inhibitory activity increases the risk of myopathy and rhabdomyolysis, particularly with higher doses of VYTORIN. [See Warnings and Precautions (5.1) and Clinical Pharmacology (12.3).] Concomitant use of drugs labeled as having a strong inhibitory effect on CYP3A4 is contraindicated [see Contraindications (4)]. If treatment with itraconazole, ketoconazole, posaconazole, erythromycin, clarithromycin or telithromycin is unavoidable, therapy with VYTORIN must be suspended during the course of treatment.

Although not studied clinically, voriconazole has been shown to inhibit lovastatin metabolism in vitro (human liver microsomes). Therefore, voriconazole is likely to increase the plasma concentration of simvastatin. It is recommended that dose adjustment of VYTORIN be considered during concomitant use of voriconazole and VYTORIN to reduce the risk of myopathy, including rhabdomyolysis. [see Warnings and Precautions (5.1)].

Cyclosporine or Danazol: The risk of myopathy, including rhabdomyolysis is increased by concomitant administration of cyclosporine or danazol. Therefore, concomitant use of these drugs is contraindicated. [see Contraindications (4), Warnings and Precautions (5.1) and Clinical Pharmacology (12.3)].

7.2 Lipid-Lowering Drugs That Can Cause Myopathy When Given Alone

Gemfibrozil: Contraindicated with VYTORIN [see Contraindications (4) and Warnings and Precautions (5.1)].

Other fibrates: Caution should be used when prescribing with VYTORIN [see Warnings and Precautions (5.1)].

7.3 Amiodarone, Ranolazine, or Calcium Channel Blockers

The risk of myopathy, including rhabdomyolysis, is increased by concomitant administration of amiodarone, ranolazine, or calcium channel blockers such as verapamil, diltiazem or amlodipine [see Dosage and Administration (2.3) and Warnings and Precautions (5.1) and Table 6 in Clinical Pharmacology (12.3)].

7.4 Niacin

Cases of myopathy/rhabdomyolysis have been observed with simvastatin coadministered with lipid-modifying doses (≥1 g/day niacin) of niacin-containing products. The benefits of the combined use of VYTORIN with niacin should be carefully weighed against the potential risks of myopathy/rhabdomyolysis. In particular, caution should be used when treating Chinese patients with VYTORIN doses exceeding 10/20 mg/day coadministered with lipid-modifying doses of niacin-containing products. Because the risk for myopathy is dose-related, Chinese patients should not receive VYTORIN 10/80 mg coadministered with lipid-modifying doses of niacin-containing products. [See Warnings and Precautions (5.1).]

7.5 Cholestyramine

Concomitant cholestyramine administration decreased the mean AUC of total ezetimibe approximately 55%. The incremental LDL-C reduction due to adding VYTORIN to cholestyramine may be reduced by this interaction.

7.6 Digoxin

In one study, concomitant administration of digoxin with simvastatin resulted in a slight elevation in plasma digoxin concentrations. Patients taking digoxin should be monitored appropriately when VYTORIN is initiated.

7.7 Fibrates

The safety and effectiveness of VYTORIN administered with fibrates have not been established. Because it is known that the risk of myopathy during treatment with HMG-CoA reductase inhibitors is increased with concurrent administration of fibrates, VYTORIN should be administered with caution when used concomitantly with fibrates (other than gemfibrozil, which is contraindicated) [see Contraindications (4) and Warnings and Precautions (5.1)].

Fibrates may increase cholesterol excretion into the bile, leading to cholelithiasis. In a preclinical study in dogs, ezetimibe increased cholesterol in the gallbladder bile [see Animal Toxicology and/or Pharmacology (13.2)].

7.8 Coumarin Anticoagulants

Simvastatin 20-40 mg/day modestly potentiated the effect of coumarin anticoagulants: the prothrombin time, reported as International Normalized Ratio (INR), increased from a baseline of 1.7 to 1.8 and from 2.6 to 3.4 in a normal volunteer study and in a hypercholesterolemic patient study, respectively. With other statins, clinically evident bleeding and/or increased prothrombin time has been reported in a few patients taking coumarin anticoagulants concomitantly. In such patients, prothrombin time should be determined before starting VYTORIN and frequently enough during early therapy to ensure that no significant alteration of prothrombin time occurs. Once a stable prothrombin time has been documented, prothrombin times can be monitored at the intervals usually recommended for patients on coumarin anticoagulants. If the dose of VYTORIN is changed or discontinued, the same procedure should be repeated. Simvastatin therapy has not been associated with bleeding or with changes in prothrombin time in patients not taking anticoagulants.

Concomitant administration of ezetimibe (10 mg once daily) had no significant effect on bioavailability of warfarin and prothrombin time in a study of twelve healthy adult males. There have been post-marketing reports of increased INR in patients who had ezetimibe added to warfarin. Most of these patients were also on other medications.

The effect of VYTORIN on the prothrombin time has not been studied.

7.9 Colchicine

Cases of myopathy, including rhabdomyolysis, have been reported with simvastatin coadministered with colchicine, and caution should be exercised when prescribing VYTORIN with colchicine.

8 USE IN SPECIFIC POPULATIONS

8.1 Pregnancy

Pregnancy Category X.

[See Contraindications (4).]

VYTORIN

VYTORIN is contraindicated in women who are or may become pregnant. Lipid-lowering drugs offer no benefit during pregnancy, because cholesterol and cholesterol derivatives are needed for normal fetal development. Atherosclerosis is a chronic process, and discontinuation of lipid-lowering drugs during pregnancy should have little impact on long-term outcomes of primary hypercholesterolemia therapy. There are no adequate and well-controlled studies of VYTORIN use during pregnancy; however, there are rare reports of congenital anomalies in infants exposed to statins in utero. Animal reproduction studies of simvastatin in rats and rabbits showed no evidence of teratogenicity. Serum cholesterol and triglycerides increase during normal pregnancy, and cholesterol or cholesterol derivatives are essential for fetal development. Because statins, such as simvastatin, decrease cholesterol synthesis and possibly the synthesis of other biologically active substances derived from cholesterol, VYTORIN may cause fetal harm when administered to a pregnant woman. If VYTORIN is used during pregnancy or if the patient becomes pregnant while taking this drug, the patient should be apprised of the potential hazard to the fetus.

Women of childbearing potential, who require VYTORIN treatment for a lipid disorder, should be advised to use effective contraception. For women trying to conceive, discontinuation of VYTORIN should be considered. If pregnancy occurs, VYTORIN should be immediately discontinued.

Ezetimibe

In oral (gavage) embryo-fetal development studies of ezetimibe conducted in rats and rabbits during organogenesis, there was no evidence of embryolethal effects at the doses tested (250, 500, 1000 mg/kg/day). In rats, increased incidences of common fetal skeletal findings (extra pair of thoracic ribs, unossified cervical vertebral centra, shortened ribs) were observed at 1000 mg/kg/day (~10 times the human exposure at 10 mg daily based on AUC0-24hr for total ezetimibe). In rabbits treated with ezetimibe, an increased incidence of extra thoracic ribs was observed at 1000 mg/kg/day (150 times the human exposure at 10 mg daily based on AUC0-24hr for total ezetimibe). Ezetimibe crossed the placenta when pregnant rats and rabbits were given multiple oral doses.

Multiple-dose studies of ezetimibe coadministered with statins in rats and rabbits during organogenesis result in higher ezetimibe and statin exposures. Reproductive findings occur at lower doses in coadministration therapy compared to monotherapy.

Simvastatin

Simvastatin was not teratogenic in rats or rabbits at doses (25, 10 mg/kg/day, respectively) that resulted in 3 times the human exposure based on mg/m^2 surface area. However, in studies with another structurally-related statin, skeletal malformations were observed in rats and mice.

There are rare reports of congenital anomalies following intrauterine exposure to statins. In a review of approximately 100 prospectively followed pregnancies in women exposed to simvastatin or another structurally-related statin, the incidences of congenital anomalies, spontaneous abortions and fetal deaths/stillbirths did not exceed what would be expected in the general population. The number of cases is adequate only to exclude a 3- to 4-fold increase in congenital anomalies over the background incidence. In 89% of the prospectively followed pregnancies, drug treatment was initiated prior to pregnancy and was discontinued at some point in the first trimester when pregnancy was identified.

8.3 Nursing Mothers

It is not known whether simvastatin is excreted in human milk. Because a small amount of another drug in this class is excreted in human milk and because of the potential for serious adverse reactions in nursing infants, women taking simvastatin should not nurse their infants. A decision should be made whether to discontinue nursing or discontinue drug, taking into account the importance of the drug to the mother [see Contraindications (4)].

In rat studies, exposure to ezetimibe in nursing pups was up to half of that observed in maternal plasma. It is not known whether ezetimibe or simvastatin are excreted into human breast milk. Because a small amount of another drug in the same class as simvastatin is excreted in human milk and because of the potential for serious adverse reactions in nursing infants, women who are nursing should not take VYTORIN [see Contraindications (4)].

8.4 Pediatric Use

The effects of ezetimibe coadministered with simvastatin (n=126) compared to simvastatin monotherapy (n=122) have been evaluated in adolescent boys and girls with heterozygous familial hypercholesterolemia (HeFH). In a multicenter, double-blind, controlled study followed by an open-label phase, 142 boys and 106 postmenarchal girls, 10 to 17 years of age (mean age 14.2 years, 43% females, 82% Caucasians, 4% Asian, 2% Blacks, 13% multiracial) with HeFH were randomized to receive either ezetimibe coadministered with simvastatin or simvastatin monotherapy. Inclusion in the study required 1) a baseline LDL-C level between 160 and 400 mg/dL and 2) a medical history and clinical presentation consistent with HeFH. The mean baseline LDL-C value was 225 mg/dL (range: 161-351 mg/dL) in the ezetimibe coadministered with simvastatin group compared to 219 mg/dL (range: 149-336 mg/dL) in the simvastatin monotherapy group. The patients received coadministered ezetimibe and simvastatin (10 mg, 20 mg, or 40 mg) or simvastatin monotherapy (10 mg, 20 mg, or 40 mg) for 6 weeks, coadministered ezetimibe and 40 mg simvastatin or 40 mg simvastatin monotherapy for the next 27 weeks, and open-label coadministered ezetimibe and simvastatin (10 mg, 20 mg, or 40 mg) for 20 weeks thereafter.

The results of the study at Week 6 are summarized in Table 3. Results at Week 33 were consistent with those at Week 6.

Table 3: Mean Percent Difference at Week 6 Between the Pooled Ezetimibe Coadministered with Simvastatin Group and the Pooled Simvastatin Monotherapy Group in Adolescent Patients with Heterozygous Familial Hypercholesterolemia
 | Total-C | LDL-C | Apo B | Non-HDL-C | TG | HDL-C
Mean percent difference between treatment groups | -12% | -15% | -12% | -14% | -2% | +0.1%
95% Confidence Interval | (-15%, -9%) | (-18%, -12%) | (-15%, -9%) | (-17%, -11%) | (-9, +4) | (-3, +3)

From the start of the trial to the end of Week 33, discontinuations due to an adverse reaction occurred in 7 (6%) patients in the ezetimibe coadministered with simvastatin group and in 2 (2%) patients in the simvastatin monotherapy group.

During the trial, hepatic transaminase elevations (two consecutive measurements for ALT and/or AST ≥3 X ULN) occurred in four (3%) individuals in the ezetimibe coadministered with simvastatin group and in two (2%) individuals in the simvastatin monotherapy group. Elevations of CPK (≥10 X ULN) occurred in two (2%) individuals in the ezetimibe coadministered with simvastatin group and in zero individuals in the simvastatin monotherapy group.

In this limited controlled study, there was no significant effect on growth or sexual maturation in the adolescent boys or girls, or on menstrual cycle length in girls.

Coadministration of ezetimibe with simvastatin at doses greater than 40 mg/day has not been studied in adolescents. Also, VYTORIN has not been studied in patients younger than 10 years of age or in pre-menarchal girls.

Ezetimibe

Based on total ezetimibe (ezetimibe + ezetimibe-glucuronide) there are no pharmacokinetic differences between adolescents and adults. Pharmacokinetic data in the pediatric population <10 years of age are not available.

Simvastatin

The pharmacokinetics of simvastatin has not been studied in the pediatric population.

8.5 Geriatric Use

Of the 10,189 patients who received VYTORIN in clinical studies, 3242 (32%) were 65 and older (this included 844 (8%) who were 75 and older). No overall differences in safety or effectiveness were observed between these subjects and younger subjects, and other reported clinical experience has not identified differences in responses between the elderly and younger patients but greater sensitivity of some older individuals cannot be ruled out. Since advanced age (≥65 years) is a predisposing factor for myopathy, VYTORIN should be prescribed with caution in the elderly. [See Clinical Pharmacology (12.3).]

Because advanced age (≥65 years) is a predisposing factor for myopathy, including rhabdomyolysis, VYTORIN should be prescribed with caution in the elderly. In a clinical trial of patients treated with simvastatin 80 mg/day, patients ≥65 years of age had an increased risk of myopathy, including rhabdomyolysis, compared to patients <65 years of age. [See Warnings and Precautions (5.1) and Clinical Pharmacology (12.3).]

8.6 Renal Impairment

In the SHARP trial of 9270 patients with moderate to severe renal impairment (6247 non-dialysis patients with median serum creatinine 2.5 mg/dL and median estimated glomerular filtration rate 25.6 mL/min/1.73 m^2, and 3023 dialysis patients), the incidence of serious adverse events, adverse events leading to discontinuation of study treatment, or adverse events of special interest (musculoskeletal adverse events, liver enzyme abnormalities, incident cancer) was similar between patients ever assigned to VYTORIN 10/20 mg (n=4650) or placebo (n=4620) during a median follow-up of 4.9 years. However, because renal impairment is a risk factor for statin-associated myopathy, doses of VYTORIN exceeding 10/20 mg should be used with caution and close monitoring in patients with moderate to severe renal impairment. [See Dosage and Administration (2.6), Adverse Reactions (6.1), and Clinical Studies (14.3).]

8.7 Hepatic Impairment

VYTORIN is contraindicated in patients with active liver disease or unexplained persistent elevations of hepatic transaminases. VYTORIN is not recommended in patients with moderate to severe hepatic impairment. [See Contraindications (4) and Warnings and Precautions (5.2).]

10 OVERDOSAGE

VYTORIN

No specific treatment of overdosage with VYTORIN can be recommended. In the event of an overdose, symptomatic and supportive measures should be employed.

Ezetimibe

In clinical studies, administration of ezetimibe, 50 mg/day to 15 healthy subjects for up to 14 days, or 40 mg/day to 18 patients with primary hyperlipidemia for up to 56 days, was generally well tolerated.

A few cases of overdosage have been reported; most have not been associated with adverse experiences. Reported adverse experiences have not been serious.

Simvastatin

Significant lethality was observed in mice after a single oral dose of 9 g/m^2. No evidence of lethality was observed in rats or dogs treated with doses of 30 and 100 g/m^2, respectively. No specific diagnostic signs were observed in rodents. At these doses the only signs seen in dogs were emesis and mucoid stools.

A few cases of overdosage with simvastatin have been reported; the maximum dose taken was 3.6 g. All patients recovered without sequelae.

The dialyzability of simvastatin and its metabolites in man is not known at present.

11 DESCRIPTION

VYTORIN contains ezetimibe, a selective inhibitor of intestinal cholesterol and related phytosterol absorption, and simvastatin, an HMG-CoA reductase inhibitor.

The chemical name of ezetimibe is 1-(4-fluorophenyl)-3(R)-[3-(4-fluorophenyl)-3(S)-hydroxypropyl]-4(S)-(4-hydroxyphenyl)-2-azetidinone. The empirical formula is C24H21F2NO3 and its molecular weight is 409.4.

Ezetimibe is a white, crystalline powder that is freely to very soluble in ethanol, methanol, and acetone and practically insoluble in water. Its structural formula is:

Simvastatin, an inactive lactone, is hydrolyzed to the corresponding β-hydroxyacid form, which is an inhibitor of HMG-CoA reductase. Simvastatin is butanoic acid, 2,2-dimethyl-,1,2,3,7,8,8a-hexahydro-3,7-dimethyl-8-[2-(tetrahydro-4-hydroxy-6-oxo-2H-pyran-2-yl)-ethyl]-1-naphthalenyl ester, [1S-[1α,3α,7β,8β(2S*,4S*),-8aβ]]. The empirical formula of simvastatin is C25H38O5 and its molecular weight is 418.57.

Simvastatin is a white to off-white, nonhygroscopic, crystalline powder that is practically insoluble in water and freely soluble in chloroform, methanol and ethanol. Its structural formula is:

VYTORIN is available for oral use as tablets containing 10 mg of ezetimibe, and 10 mg of simvastatin (VYTORIN 10/10), 20 mg of simvastatin (VYTORIN 10/20), 40 mg of simvastatin (VYTORIN 10/40), or 80 mg of simvastatin (VYTORIN 10/80). Each tablet contains the following inactive ingredients: butylated hydroxyanisole NF, citric acid monohydrate USP, croscarmellose sodium NF, hypromellose USP, lactose monohydrate NF, magnesium stearate NF, microcrystalline cellulose NF, and propyl gallate NF.

12 CLINICAL PHARMACOLOGY

12.1 Mechanism of Action

VYTORIN

Plasma cholesterol is derived from intestinal absorption and endogenous synthesis. VYTORIN contains ezetimibe and simvastatin, two lipid-lowering compounds with complementary mechanisms of action. VYTORIN reduces elevated total-C, LDL-C, Apo B, TG, and non-HDL-C, and increases HDL-C through dual inhibition of cholesterol absorption and synthesis.

Ezetimibe

Ezetimibe reduces blood cholesterol by inhibiting the absorption of cholesterol by the small intestine. The molecular target of ezetimibe has been shown to be the sterol transporter, Niemann-Pick C1-Like 1 (NPC1L1), which is involved in the intestinal uptake of cholesterol and phytosterols. In a 2-week clinical study in 18 hypercholesterolemic patients, ezetimibe inhibited intestinal cholesterol absorption by 54%, compared with placebo. Ezetimibe had no clinically meaningful effect on the plasma concentrations of the fat-soluble vitamins A, D, and E and did not impair adrenocortical steroid hormone production.

Ezetimibe localizes at the brush border of the small intestine and inhibits the absorption of cholesterol, leading to a decrease in the delivery of intestinal cholesterol to the liver. This causes a reduction of hepatic cholesterol stores and an increase in clearance of cholesterol from the blood; this distinct mechanism is complementary to that of statins [see Clinical Studies (14)].

Simvastatin

Simvastatin is a prodrug and is hydrolyzed to its active β-hydroxyacid form, simvastatin acid, after administration. Simvastatin is a specific inhibitor of 3-hydroxy-3-methylglutaryl-coenzyme A (HMG-CoA) reductase, the enzyme that catalyzes the conversion of HMG-CoA to mevalonate, an early and rate limiting step in the biosynthetic pathway for cholesterol. In addition, simvastatin reduces very-low-density lipoproteins (VLDL) and TG and increases HDL-C.

12.2 Pharmacodynamics

Clinical studies have demonstrated that elevated levels of total-C, LDL-C and Apo B, the major protein constituent of LDL, promote human atherosclerosis. In addition, decreased levels of HDL-C are associated with the development of atherosclerosis. Epidemiologic studies have established that cardiovascular morbidity and mortality vary directly with the level of total-C and LDL-C and inversely with the level of HDL-C. Like LDL, cholesterol-enriched triglyceride-rich lipoproteins, including VLDL, intermediate-density lipoproteins (IDL), and remnants, can also promote atherosclerosis. The independent effect of raising HDL-C or lowering TG on the risk of coronary and cardiovascular morbidity and mortality has not been determined.

12.3 Pharmacokinetics

The results of a bioequivalence study in healthy subjects demonstrated that the VYTORIN (ezetimibe/simvastatin) 10 mg/10 mg to 10 mg/80 mg combination tablets are bioequivalent to coadministration of corresponding doses of ezetimibe (ZETIA®) and simvastatin (ZOCOR®) as individual tablets.

Absorption

Ezetimibe

After oral administration, ezetimibe is absorbed and extensively conjugated to a pharmacologically active phenolic glucuronide (ezetimibe-glucuronide).

Simvastatin

The availability of the β-hydroxyacid to the systemic circulation following an oral dose of simvastatin was found to be less than 5% of the dose, consistent with extensive hepatic first-pass extraction.

Effect of Food on Oral Absorption

Ezetimibe

Concomitant food administration (high-fat or non-fat meals) had no effect on the extent of absorption of ezetimibe when administered as 10-mg tablets. The Cmax value of ezetimibe was increased by 38% with consumption of high-fat meals.

Simvastatin

Relative to the fasting state, the plasma profiles of both active and total inhibitors of HMG-CoA reductase were not affected when simvastatin was administered immediately before an American Heart Association recommended low-fat meal.

Distribution

Ezetimibe

Ezetimibe and ezetimibe-glucuronide are highly bound (>90%) to human plasma proteins.

Simvastatin

Both simvastatin and its β-hydroxyacid metabolite are highly bound (approximately 95%) to human plasma proteins. When radiolabeled simvastatin was administered to rats, simvastatin-derived radioactivity crossed the blood-brain barrier.

Metabolism and Excretion

Ezetimibe

Ezetimibe is primarily metabolized in the small intestine and liver via glucuronide conjugation with subsequent biliary and renal excretion. Minimal oxidative metabolism has been observed in all species evaluated.

In humans, ezetimibe is rapidly metabolized to ezetimibe-glucuronide. Ezetimibe and ezetimibe-glucuronide are the major drug-derived compounds detected in plasma, constituting approximately 10 to 20% and 80 to 90% of the total drug in plasma, respectively. Both ezetimibe and ezetimibe-glucuronide are eliminated from plasma with a half-life of approximately 22 hours for both ezetimibe and ezetimibe-glucuronide. Plasma concentration-time profiles exhibit multiple peaks, suggesting enterohepatic recycling.

Following oral administration of ^14C-ezetimibe (20 mg) to human subjects, total ezetimibe (ezetimibe + ezetimibe-glucuronide) accounted for approximately 93% of the total radioactivity in plasma. After 48 hours, there were no detectable levels of radioactivity in the plasma.

Approximately 78% and 11% of the administered radioactivity were recovered in the feces and urine, respectively, over a 10-day collection period. Ezetimibe was the major component in feces and accounted for 69% of the administered dose, while ezetimibe-glucuronide was the major component in urine and accounted for 9% of the administered dose.

Simvastatin

Simvastatin is a lactone that is readily hydrolyzed in vivo to the corresponding β-hydroxyacid, a potent inhibitor of HMG-CoA reductase. Inhibition of HMG-CoA reductase is a basis for an assay in pharmacokinetic studies of the β-hydroxyacid metabolites (active inhibitors) and, following base hydrolysis, active plus latent inhibitors (total inhibitors) in plasma following administration of simvastatin. The major active metabolites of simvastatin present in human plasma are the β-hydroxyacid of simvastatin and its 6'-hydroxy, 6'-hydroxymethyl, and 6'-exomethylene derivatives.

Following an oral dose of ^14C-labeled simvastatin in man, 13% of the dose was excreted in urine and 60% in feces. Plasma concentrations of total radioactivity (simvastatin plus ^14C-metabolites) peaked at 4 hours and declined rapidly to about 10% of peak by 12 hours postdose.

Specific Populations

Geriatric Patients

Ezetimibe

In a multiple-dose study with ezetimibe given 10 mg once daily for 10 days, plasma concentrations for total ezetimibe were about 2-fold higher in older (≥65 years) healthy subjects compared to younger subjects.

Simvastatin

In a study including 16 elderly patients between 70 and 78 years of age who received simvastatin 40 mg/day, the mean plasma level of HMG-CoA reductase inhibitory activity was increased approximately 45% compared with 18 patients between 18-30 years of age.

Pediatric Patients: [See Pediatric Use (8.4).]

Gender

Ezetimibe

In a multiple-dose study with ezetimibe given 10 mg once daily for 10 days, plasma concentrations for total ezetimibe were slightly higher (<20%) in women than in men.

Race

Ezetimibe

Based on a meta-analysis of multiple-dose pharmacokinetic studies, there were no pharmacokinetic differences between Black and Caucasian subjects. Studies in Asian subjects indicated that the pharmacokinetics of ezetimibe was similar to those seen in Caucasian subjects.

Hepatic Impairment

Ezetimibe

After a single 10-mg dose of ezetimibe, the mean exposure (based on area under the curve [AUC]) to total ezetimibe was increased approximately 1.7-fold in patients with mild hepatic impairment (Child-Pugh score 5 to 6), compared to healthy subjects. The mean AUC values for total ezetimibe and ezetimibe increased approximately 3- to 4-fold and 5- to 6-fold, respectively, in patients with moderate (Child-Pugh score 7 to 9) or severe hepatic impairment (Child-Pugh score 10 to 15). In a 14-day, multiple-dose study (10 mg daily) in patients with moderate hepatic impairment, the mean AUC for total ezetimibe and ezetimibe increased approximately 4-fold compared to healthy subjects.

Renal Impairment

Ezetimibe

After a single 10-mg dose of ezetimibe in patients with severe renal disease (n=8; mean CrCl ≤30 mL/min/1.73 m^2), the mean AUC for total ezetimibe and ezetimibe increased approximately 1.5-fold, compared to healthy subjects (n=9).

Simvastatin

Pharmacokinetic studies with another statin having a similar principal route of elimination to that of simvastatin have suggested that for a given dose level higher systemic exposure may be achieved in patients with severe renal impairment (as measured by creatinine clearance).

Drug Interactions [See also Drug Interactions (7).]

No clinically significant pharmacokinetic interaction was seen when ezetimibe was coadministered with simvastatin. No specific pharmacokinetic drug interaction studies with VYTORIN have been conducted other than the following study with NIASPAN (Niacin extended-release tablets).

Niacin: The effect of VYTORIN (10/20 mg daily for 7 days) on the pharmacokinetics of NIASPAN extended-release tablets (1000 mg for 2 days and 2000 mg for 5 days following a low-fat breakfast) was studied in healthy subjects. The mean Cmax and AUC of niacin increased 9% and 22%, respectively. The mean Cmax and AUC of nicotinuric acid increased 10% and 19%, respectively (N=13). In the same study, the effect of NIASPAN on the pharmacokinetics of VYTORIN was evaluated (N=15). While concomitant NIASPAN decreased the mean Cmax of total ezetimibe (1%), and simvastatin (2%), it increased the mean Cmax of simvastatin acid (18%). In addition, concomitant NIASPAN increased the mean AUC of total ezetimibe (26%), simvastatin (20%), and simvastatin acid (35%).

Cases of myopathy/rhabdomyolysis have been observed with simvastatin coadministered with lipid-modifying doses (≥1 g/day niacin) of niacin-containing products. [See Warnings and Precautions (5.1) and Drug Interactions (7.4).]

Cytochrome P450: Ezetimibe had no significant effect on a series of probe drugs (caffeine, dextromethorphan, tolbutamide, and IV midazolam) known to be metabolized by cytochrome P450 (1A2, 2D6, 2C8/9 and 3A4) in a "cocktail" study of twelve healthy adult males. This indicates that ezetimibe is neither an inhibitor nor an inducer of these cytochrome P450 isozymes, and it is unlikely that ezetimibe will affect the metabolism of drugs that are metabolized by these enzymes.

In a study of 12 healthy volunteers, simvastatin at the 80-mg dose had no effect on the metabolism of the probe cytochrome P450 isoform 3A4 (CYP3A4) substrates midazolam and erythromycin. This indicates that simvastatin is not an inhibitor of CYP3A4 and, therefore, is not expected to affect the plasma levels of other drugs metabolized by CYP3A4.

Although the mechanism is not fully understood, cyclosporine has been shown to increase the AUC of statins. The increase in AUC for simvastatin acid is presumably due, in part, to inhibition of CYP3A4.

Simvastatin is a substrate for CYP3A4. Inhibitors of CYP3A4 can raise the plasma levels of HMG-CoA reductase inhibitory activity and increase the risk of myopathy. [See Warnings and Precautions (5.1); Drug Interactions (7.1).]

Ezetimibe

Table 4: Effect of Coadministered Drugs on Total Ezetimibe
Coadministered Drug and Dosing Regimen | Total Ezetimibe
Coadministered Drug and Dosing Regimen | Change in AUC | Change in Cmax
Cyclosporine-stable dose required (75-150 mg BID), [See 7. Drug Interactions] | ↑240% | ↑290%
Fenofibrate, 200 mg QD, 14 days | ↑48% | ↑64%
Gemfibrozil, 600 mg BID, 7 days | ↑64% | ↑91%
Cholestyramine, 4 g BID, 14 days | ↓55% | ↓4%
Aluminum & magnesium hydroxide combination antacid, single dose | ↓4% | ↓30%
Cimetidine, 400 mg BID, 7 days | ↑6% | ↑22%
Glipizide, 10 mg, single dose | ↑4% | ↓8%
Statins
Lovastatin 20 mg QD, 7 days | ↑9% | ↑3%
Pravastatin 20 mg QD, 14 days | ↑7% | ↑23%
Atorvastatin 10 mg QD, 14 days | ↓2% | ↑12%
Rosuvastatin 10 mg QD, 14 days | ↑13% | ↑18%
Fluvastatin 20 mg QD, 14 days | ↓19% | ↑7%

Table 5: Effect of Ezetimibe Coadministration on Systemic Exposure to Other Drugs
Coadministered Drug and its Dosage Regimen | Ezetimibe Dosage Regimen | Change in AUC; of Coadministered Drug | Change in Cmax; of Coadministered Drug
Warfarin, 25 mg single dose on Day 7 | 10 mg QD, 11 days | ↓2% (R-warfarin); ↓4% (S-warfarin) | ↑3% (R-warfarin); ↑1% (S-warfarin)
Digoxin, 0.5 mg single dose | 10 mg QD, 8 days | ↑2% | ↓7%
Gemfibrozil, 600 mg BID, 7 days [See 7. Drug Interactions] | 10 mg QD, 7 days | ↓1% | ↓11%
Ethinyl estradiol & Levonorgestrel, QD, 21 days | 10 mg QD, Days 8-14 of 21 day oral contraceptive cycle | Ethinyl estradiol; 0%; Levonorgestrel; 0% | Ethinyl estradiol; ↓9%; Levonorgestrel; ↓5%
Glipizide, 10 mg on Days 1 and 9 | 10 mg QD, Days 2-9 | ↓3% | ↓5%
Fenofibrate, 200 mg QD, 14 days | 10 mg QD, 14 days | ↑11% | ↑7%
Cyclosporine, 100 mg single dose Day 7 | 20 mg QD, 8 days | ↑15% | ↑10%
Statins
Lovastatin 20 mg QD, 7 days | 10 mg QD, 7 days | ↑19% | ↑3%
Pravastatin 20 mg QD, 14 days | 10 mg QD, 14 days | ↓20% | ↓24%
Atorvastatin 10 mg QD, 14 days | 10 mg QD, 14 days | ↓4% | ↑7%
Rosuvastatin 10 mg QD, 14 days | 10 mg QD, 14 days | ↑19% | ↑17%
Fluvastatin 20 mg QD, 14 days | 10 mg QD, 14 days | ↓39% | ↓27%

Simvastatin

Table 6: Effect of Coadministered Drugs or Grapefruit Juice on Simvastatin Systemic Exposure
Coadministered Drug or Grapefruit Juice | Dosing of Coadministered Drug or Grapefruit Juice | Dosing of Simvastatin | Geometric Mean Ratio; (Ratio with / without coadministered drug); No Effect = 1.00
Coadministered Drug or Grapefruit Juice | Dosing of Coadministered Drug or Grapefruit Juice | Dosing of Simvastatin |  | AUC | Cmax
Contraindicated with VYTORIN [see Contraindications (4) and Warnings and Precautions (5.1)]
Telithromycin [Results could be representative of the following CYP3A4 inhibitors: ketoconazole, erythromycin, clarithromycin, HIV protease inhibitors, and nefazodone.] | 200 mg QD for 4 days | 80 mg | simvastatin acid [Simvastatin acid refers to the β-hydroxyacid of simvastatin.] simvastatin | 12 8.9 | 15 5.3
Nelfinavir | 1250 mg BID for 14 days | 20 mg QD for 28 days | simvastatin acid simvastatin | 6 | 6.2
Itraconazole | 200 mg QD for 4 days | 80 mg | simvastatin acid simvastatin |  | 13.1; 13.1
Posaconazole | 100 mg (oral suspension) QD for 13 days 200 mg (oral suspension) QD for 13 days | 40 mg; 40 mg | simvastatin acid simvastatin simvastatin acid; simvastatin | 7.3 10.3; 8.5 10.6 | 9.2 9.4; 9.5 11.4
Gemfibrozil | 600 mg BID for 3 days | 40 mg | simvastatin acid simvastatin | 2.85; 1.35 | 2.18; 0.91
Avoid >1 quart of grapefruit juice with VYTORIN [see Warnings and Precautions (5.1)]
Grapefruit Juice [The effect of amounts of grapefruit juice between those used in these two studies on simvastatin pharmacokinetics has not been studied.]; (high dose) | 200 mL of double-strength TID | 60 mg single dose | simvastatin acid simvastatin | 7 16
Grapefruit Juice; (low dose) | 8 oz (about 237 mL) of single-strength | 20 mg single dose | simvastatin acid simvastatin | 1.3 1.9
Avoid taking with >10/10 mg VYTORIN, based on clinical and/or post-marketing simvastatin experience [see Warnings and Precautions (5.1)]
Verapamil SR | 240 mg QD Days 1-7 then 240 mg BID on Days 8-10 | 80 mg on Day 10 | simvastatin acid simvastatin | 2.3 2.5 | 2.4 2.1
Diltiazem | 120 mg BID for 10 days | 80 mg on Day 10 | simvastatin acid simvastatin | 2.69 3.10 | 2.69 2.88
Diltiazem | 120 mg BID for 14 days | 20 mg on Day 14 | simvastatin | 4.6 | 3.6
Avoid taking with >10/20 mg VYTORIN, based on clinical and/or post-marketing simvastatin experience [see Warnings and Precautions (5.1)]
Amiodarone | 400 mg QD for 3 days | 40 mg on Day 3 | simvastatin acid simvastatin | 1.75 1.76 | 1.72 1.79
Amlodipine | 10 mg QD for 10 days | 80 mg on Day 10 | simvastatin acid simvastatin | 1.58 1.77 | 1.56 1.47
Ranolazine SR | 1000 mg BID for 7 days | 80 mg on Day 1 and Days 6-9 | simvastatin acid simvastatin | 2.26 1.86 | 2.28 1.75
No dosing adjustments required for the following:
Fenofibrate | 160 mg QD for 14 days | 80 mg QD on Days 8-14 | simvastatin acid simvastatin | 0.64 0.89 | 0.89 0.83
Propranolol | 80 mg single dose | 80 mg single dose | total inhibitor active inhibitor | 0.79 0.79 | ↓ from 33.6 to 21.1 ng∙eq/mL ↓ from 7.0 to 4.7 ng∙eq/mL

13 NONCLINICAL TOXICOLOGY

13.1 Carcinogenesis, Mutagenesis, Impairment of Fertility

VYTORIN

No animal carcinogenicity or fertility studies have been conducted with the combination of ezetimibe and simvastatin. The combination of ezetimibe with simvastatin did not show evidence of mutagenicity in vitro in a microbial mutagenicity (Ames) test with Salmonella typhimurium and Escherichia coli with or without metabolic activation. No evidence of clastogenicity was observed in vitro in a chromosomal aberration assay in human peripheral blood lymphocytes with ezetimibe and simvastatin with or without metabolic activation. There was no evidence of genotoxicity at doses up to 600 mg/kg with the combination of ezetimibe and simvastatin (1:1) in the in vivo mouse micronucleus test.

Ezetimibe

A 104-week dietary carcinogenicity study with ezetimibe was conducted in rats at doses up to 1500 mg/kg/day (males) and 500 mg/kg/day (females) (~20 times the human exposure at 10 mg daily based on AUC0-24hr for total ezetimibe). A 104-week dietary carcinogenicity study with ezetimibe was also conducted in mice at doses up to 500 mg/kg/day (>150 times the human exposure at 10 mg daily based on AUC0-24hr for total ezetimibe). There were no statistically significant increases in tumor incidences in drug-treated rats or mice.

No evidence of mutagenicity was observed in vitro in a microbial mutagenicity (Ames) test with Salmonella typhimurium and Escherichia coli with or without metabolic activation. No evidence of clastogenicity was observed in vitro in a chromosomal aberration assay in human peripheral blood lymphocytes with or without metabolic activation. In addition, there was no evidence of genotoxicity in the in vivo mouse micronucleus test.

In oral (gavage) fertility studies of ezetimibe conducted in rats, there was no evidence of reproductive toxicity at doses up to 1000 mg/kg/day in male or female rats (~7 times the human exposure at 10 mg daily based on AUC0-24hr for total ezetimibe).

Simvastatin

In a 72-week carcinogenicity study, mice were administered daily doses of simvastatin of 25, 100, and 400 mg/kg body weight, which resulted in mean plasma drug levels approximately 1, 4, and 8 times higher than the mean human plasma drug level, respectively, (as total inhibitory activity based on AUC) after an 80-mg oral dose. Liver carcinomas were significantly increased in high-dose females and mid- and high-dose males with a maximum incidence of 90% in males. The incidence of adenomas of the liver was significantly increased in mid- and high-dose females. Drug treatment also significantly increased the incidence of lung adenomas in mid- and high-dose males and females. Adenomas of the Harderian gland (a gland of the eye of rodents) were significantly higher in high-dose mice than in controls. No evidence of a tumorigenic effect was observed at 25 mg/kg/day.

In a separate 92-week carcinogenicity study in mice at doses up to 25 mg/kg/day, no evidence of a tumorigenic effect was observed (mean plasma drug levels were 1 times higher than humans given 80 mg simvastatin as measured by AUC).

In a two-year study in rats at 25 mg/kg/day, there was a statistically significant increase in the incidence of thyroid follicular adenomas in female rats exposed to approximately 11 times higher levels of simvastatin than in humans given 80 mg simvastatin (as measured by AUC).

A second two-year rat carcinogenicity study with doses of 50 and 100 mg/kg/day produced hepatocellular adenomas and carcinomas (in female rats at both doses and in males at 100 mg/kg/day). Thyroid follicular cell adenomas were increased in males and females at both doses; thyroid follicular cell carcinomas were increased in females at 100 mg/kg/day. The increased incidence of thyroid neoplasms appears to be consistent with findings from other statins. These treatment levels represented plasma drug levels (AUC) of approximately 7 and 15 times (males) and 22 and 25 times (females) the mean human plasma drug exposure after an 80-mg daily dose.

No evidence of mutagenicity was observed in a microbial mutagenicity (Ames) test with or without rat or mouse liver metabolic activation. In addition, no evidence of damage to genetic material was noted in an in vitro alkaline elution assay using rat hepatocytes, a V-79 mammalian cell forward mutation study, an in vitro chromosome aberration study in CHO cells, or an in vivo chromosomal aberration assay in mouse bone marrow.

There was decreased fertility in male rats treated with simvastatin for 34 weeks at 25 mg/kg body weight (4 times the maximum human exposure level, based on AUC, in patients receiving 80 mg/day); however, this effect was not observed during a subsequent fertility study in which simvastatin was administered at this same dose level to male rats for 11 weeks (the entire cycle of spermatogenesis including epididymal maturation). No microscopic changes were observed in the testes of rats from either study. At 180 mg/kg/day (which produces exposure levels 22 times higher than those in humans taking 80 mg/day based on surface area, mg/m^2), seminiferous tubule degeneration (necrosis and loss of spermatogenic epithelium) was observed. In dogs, there was drug-related testicular atrophy, decreased spermatogenesis, spermatocytic degeneration and giant cell formation at 10 mg/kg/day (approximately 2 times the human exposure, based on AUC, at 80 mg/day). The clinical significance of these findings is unclear.

13.2 Animal Toxicology and/or Pharmacology

CNS Toxicity

Optic nerve degeneration was seen in clinically normal dogs treated with simvastatin for 14 weeks at 180 mg/kg/day, a dose that produced mean plasma drug levels about 12 times higher than the mean plasma drug level in humans taking 80 mg/day.

A chemically similar drug in this class also produced optic nerve degeneration (Wallerian degeneration of retinogeniculate fibers) in clinically normal dogs in a dose-dependent fashion starting at 60 mg/kg/day, a dose that produced mean plasma drug levels about 30 times higher than the mean plasma drug level in humans taking the highest recommended dose (as measured by total enzyme inhibitory activity). This same drug also produced vestibulocochlear Wallerian-like degeneration and retinal ganglion cell chromatolysis in dogs treated for 14 weeks at 180 mg/kg/day, a dose that resulted in a mean plasma drug level similar to that seen with the 60 mg/kg/day dose.

CNS vascular lesions, characterized by perivascular hemorrhage and edema, mononuclear cell infiltration of perivascular spaces, perivascular fibrin deposits and necrosis of small vessels, were seen in dogs treated with simvastatin at a dose of 360 mg/kg/day, a dose that produced mean plasma drug levels that were about 14 times higher than the mean plasma drug levels in humans taking 80 mg/day. Similar CNS vascular lesions have been observed with several other drugs of this class.

There were cataracts in female rats after two years of treatment with 50 and 100 mg/kg/day (22 and 25 times the human AUC at 80 mg/day, respectively) and in dogs after three months at 90 mg/kg/day (19 times) and at two years at 50 mg/kg/day (5 times).

Ezetimibe

The hypocholesterolemic effect of ezetimibe was evaluated in cholesterol-fed Rhesus monkeys, dogs, rats, and mouse models of human cholesterol metabolism. Ezetimibe was found to have an ED50 value of 0.5 μg/kg/day for inhibiting the rise in plasma cholesterol levels in monkeys. The ED50 values in dogs, rats, and mice were 7, 30, and 700 μg/kg/day, respectively. These results are consistent with ezetimibe being a potent cholesterol absorption inhibitor.

In a rat model, where the glucuronide metabolite of ezetimibe (ezetimibe-glucuronide) was administered intraduodenally, the metabolite was as potent as ezetimibe in inhibiting the absorption of cholesterol, suggesting that the glucuronide metabolite had activity similar to the parent drug.

In 1-month studies in dogs given ezetimibe (0.03 to 300 mg/kg/day), the concentration of cholesterol in gallbladder bile increased ~2- to 4-fold. However, a dose of 300 mg/kg/day administered to dogs for one year did not result in gallstone formation or any other adverse hepatobiliary effects. In a 14-day study in mice given ezetimibe (0.3 to 5 mg/kg/day) and fed a low-fat or cholesterol-rich diet, the concentration of cholesterol in gallbladder bile was either unaffected or reduced to normal levels, respectively.

A series of acute preclinical studies was performed to determine the selectivity of ezetimibe for inhibiting cholesterol absorption. Ezetimibe inhibited the absorption of ^14C-cholesterol with no effect on the absorption of triglycerides, fatty acids, bile acids, progesterone, ethinyl estradiol, or the fat-soluble vitamins A and D.

In 4- to 12-week toxicity studies in mice, ezetimibe did not induce cytochrome P450 drug-metabolizing enzymes. In toxicity studies, a pharmacokinetic interaction of ezetimibe with statins (parents or their active hydroxy acid metabolites) was seen in rats, dogs, and rabbits.

14 CLINICAL STUDIES

14.1 Primary Hyperlipidemia

VYTORIN

VYTORIN reduces total-C, LDL-C, Apo B, TG, and non-HDL-C, and increases HDL-C in patients with hyperlipidemia. Maximal to near maximal response is generally achieved within 2 weeks and maintained during chronic therapy.

VYTORIN is effective in men and women with hyperlipidemia. Experience in non-Caucasians is limited and does not permit a precise estimate of the magnitude of the effects of VYTORIN.

Five multicenter, double-blind studies conducted with either VYTORIN or coadministered ezetimibe and simvastatin equivalent to VYTORIN in patients with primary hyperlipidemia are reported: two were comparisons with simvastatin, two were comparisons with atorvastatin, and one was a comparison with rosuvastatin.

In a multicenter, double-blind, placebo-controlled, 12-week trial, 1528 hyperlipidemic patients were randomized to one of ten treatment groups: placebo, ezetimibe (10 mg), simvastatin (10 mg, 20 mg, 40 mg, or 80 mg), or VYTORIN (10/10, 10/20, 10/40, or 10/80).

When patients receiving VYTORIN were compared to those receiving all doses of simvastatin, VYTORIN significantly lowered total-C, LDL-C, Apo B, TG, and non-HDL-C. The effects of VYTORIN on HDL-C were similar to the effects seen with simvastatin. Further analysis showed VYTORIN significantly increased HDL-C compared with placebo. (See Table 7.) The lipid response to VYTORIN was similar in patients with TG levels greater than or less than 200 mg/dL.

Table 7: Response to VYTORIN in Patients with Primary Hyperlipidemia (Mean [For triglycerides, median % change from baseline] % Change from Untreated Baseline)
Treatment (Daily Dose) | N | Total-C | LDL-C | Apo B | HDL-C | TG | Non-HDL-C
Pooled data (All VYTORIN doses) [VYTORIN doses pooled (10/10-10/80) significantly reduced total-C, LDL-C, Apo B, TG, and non-HDL-C compared to simvastatin and significantly increased HDL-C compared to placebo.] | 609 | -38 | -53 | -42 | +7 | -24 | -49
Pooled data (All simvastatin doses) | 622 | -28 | -39 | -32 | +7 | -21 | -36
Ezetimibe 10 mg | 149 | -13 | -19 | -15 | +5 | -11 | -18
Placebo | 148 | -1 | -2 | 0 | 0 | -2 | -2
VYTORIN by dose
10/10 | 152 | -31 | -45 | -35 | +8 | -23 | -41
10/20 | 156 | -36 | -52 | -41 | +10 | -24 | -47
10/40 | 147 | -39 | -55 | -44 | +6 | -23 | -51
10/80 | 154 | -43 | -60 | -49 | +6 | -31 | -56
Simvastatin by dose
10 mg | 158 | -23 | -33 | -26 | +5 | -17 | -30
20 mg | 150 | -24 | -34 | -28 | +7 | -18 | -32
40 mg | 156 | -29 | -41 | -33 | +8 | -21 | -38
80 mg | 158 | -35 | -49 | -39 | +7 | -27 | -45

In a multicenter, double-blind, controlled, 23-week study, 710 patients with known CHD or CHD risk equivalents, as defined by the NCEP ATP III guidelines, and an LDL-C ≥130 mg/dL were randomized to one of four treatment groups: coadministered ezetimibe and simvastatin equivalent to VYTORIN (10/10, 10/20, and 10/40) or simvastatin 20 mg. Patients not reaching an LDL-C <100 mg/dL had their simvastatin dose titrated at 6-week intervals to a maximal dose of 80 mg.

At Week 5, the LDL-C reductions with VYTORIN 10/10, 10/20, or 10/40 were significantly larger than with simvastatin 20 mg (see Table 8).

Table 8: Response to VYTORIN after 5 Weeks in Patients with CHD or CHD Risk Equivalents and an LDL-C ≥130 mg/dL
 | Simvastatin 20 mg | VYTORIN 10/10 | VYTORIN 10/20 | VYTORIN 10/40
N | 253 | 251 | 109 | 97
Mean baseline LDL-C | 174 | 165 | 167 | 171
Percent change LDL-C | -38 | -47 | -53 | -59

In a multicenter, double-blind, 6-week study, 1902 patients with primary hyperlipidemia, who had not met their NCEP ATP III target LDL-C goal, were randomized to one of eight treatment groups: VYTORIN (10/10, 10/20, 10/40, or 10/80) or atorvastatin (10 mg, 20 mg, 40 mg, or 80 mg).

Across the dosage range, when patients receiving VYTORIN were compared to those receiving milligram-equivalent statin doses of atorvastatin, VYTORIN lowered total-C, LDL-C, Apo B, and non-HDL-C significantly more than atorvastatin. Only the 10/40 mg and 10/80 mg VYTORIN doses increased HDL-C significantly more than the corresponding milligram-equivalent statin dose of atorvastatin. The effects of VYTORIN on TG were similar to the effects seen with atorvastatin. (See Table 9.)

Table 9: Response to VYTORIN and Atorvastatin in Patients with Primary Hyperlipidemia (Mean [For triglycerides, median % change from baseline] % Change from Untreated Baseline)
Treatment (Daily Dose) | N | Total-C [VYTORIN doses pooled (10/10-10/80) provided significantly greater reductions in total-C, LDL-C, Apo B, and non-HDL-C compared to atorvastatin doses pooled (10-80).] | LDL-C | Apo B | HDL-C | TG | Non-HDL-C
VYTORIN by dose
10/10 | 230 | -34 [p<0.05 for difference with atorvastatin at equal mg doses of the simvastatin component] | -47 | -37 | +8 | -26 | -43
10/20 | 233 | -37 | -51 | -40 | +7 | -25 | -46
10/40 | 236 | -41 | -57 | -46 | +9 | -27 | -52
10/80 | 224 | -43 | -59 | -48 | +8 | -31 | -54
Atorvastatin by dose
10 mg | 235 | -27 | -36 | -31 | +7 | -21 | -34
20 mg | 230 | -32 | -44 | -37 | +5 | -25 | -41
40 mg | 232 | -36 | -48 | -40 | +4 | -24 | -45
80 mg | 230 | -40 | -53 | -44 | +1 | -32 | -50

In a multicenter, double-blind, 24-week, forced-titration study, 788 patients with primary hyperlipidemia, who had not met their NCEP ATP III target LDL-C goal, were randomized to receive coadministered ezetimibe and simvastatin equivalent to VYTORIN (10/10 and 10/20) or atorvastatin 10 mg. For all three treatment groups, the dose of the statin was titrated at 6-week intervals to 80 mg. At each pre-specified dose comparison, VYTORIN lowered LDL-C to a greater degree than atorvastatin (see Table 10).

Table 10: Response to VYTORIN and Atorvastatin in Patients with Primary Hyperlipidemia (Mean [For triglycerides, median % change from baseline] % Change from Untreated Baseline)
Treatment | N | Total-C | LDL-C | Apo B | HDL-C | TG | Non-HDL-C
Week 6
Atorvastatin 10 mg | 262 | -28 | -37 | -32 | +5 | -23 | -35
VYTORIN10/10 | 263 | -34 [p≤0.05 for difference with atorvastatin in the specified week] | -46 | -38 | +8 | -26 | -43
VYTORIN 10/20 | 263 | -36 | -50 | -41 | +10 | -25 | -46
Week 12
Atorvastatin 20 mg | 246 | -33 | -44 | -38 | +7 | -28 | -42
VYTORIN 10/20 | 250 | -37 | -50 | -41 | +9 | -28 | -46
VYTORIN 10/40 | 252 | -39 | -54 | -45 | +12 | -31 | -50
Week 18
Atorvastatin 40 mg | 237 | -37 | -49 | -42 | +8 | -31 | -47
VYTORIN 10/40 [Data pooled for common doses of VYTORIN at Weeks 18 and 24.] | 482 | -40 | -56 | -45 | +11 | -32 | -52
Week 24
Atorvastatin 80 mg | 228 | -40 | -53 | -45 | +6 | -35 | -50
VYTORIN 10/80 | 459 | -43 | -59 | -49 | +12 | -35 | -55

In a multicenter, double-blind, 6-week study, 2959 patients with primary hyperlipidemia, who had not met their NCEP ATP III target LDL-C goal, were randomized to one of six treatment groups: VYTORIN (10/20, 10/40, or 10/80) or rosuvastatin (10 mg, 20 mg, or 40 mg).

The effects of VYTORIN and rosuvastatin on total-C, LDL-C, Apo B, TG, non-HDL-C and HDL-C are shown in Table 11.

Table 11: Response to VYTORIN and Rosuvastatin in Patients with Primary Hyperlipidemia (Mean [For triglycerides, median % change from baseline] % Change from Untreated Baseline)
Treatment (Daily Dose) | N | Total-C [VYTORIN doses pooled (10/20-10/80) provided significantly greater reductions in total-C, LDL-C, Apo B, and non-HDL-C compared to rosuvastatin doses pooled (10-40 mg).] | LDL-C | Apo B | HDL-C | TG | Non-HDL-C
VYTORIN by dose 10/20 | 476 | -37 [p<0.05 vs. rosuvastatin 10 mg] | -52 | -42 | +7 | -23 | -47
10/40 | 477 | -39 [p<0.05 vs. rosuvastatin 20 mg] | -55 | -44 | +8 | -27 | -50
10/80 | 474 | -44 [p<0.05 vs. rosuvastatin 40 mg] | -61 | -50 | +8 | -30 | -56
Rosuvastatin by dose 10 mg | 475 | -32 | -46 | -37 | +7 | -20 | -42
20 mg | 478 | -37 | -52 | -43 | +8 | -26 | -48
40 mg | 475 | -41 | -57 | -47 | +8 | -28 | -52

In a multicenter, double-blind, 24-week trial, 214 patients with type 2 diabetes mellitus treated with thiazolidinediones (rosiglitazone or pioglitazone) for a minimum of 3 months and simvastatin 20 mg for a minimum of 6 weeks were randomized to receive either simvastatin 40 mg or the coadministered active ingredients equivalent to VYTORIN 10/20. The median LDL-C and HbA1c levels at baseline were 89 mg/dL and 7.1%, respectively.

VYTORIN 10/20 was significantly more effective than doubling the dose of simvastatin to 40 mg. The median percent changes from baseline for VYTORIN vs. simvastatin were: LDL-C -25% and -5%; total-C -16% and -5%; Apo B -19% and -5%; and non-HDL-C -23% and -5%. Results for HDL-C and TG between the two treatment groups were not significantly different.

Ezetimibe

In two multicenter, double-blind, placebo-controlled, 12-week studies in 1719 patients with primary hyperlipidemia, ezetimibe significantly lowered total-C (-13%), LDL-C (-19%), Apo B (-14%), and TG (-8%), and increased HDL-C (+3%) compared to placebo. Reduction in LDL-C was consistent across age, sex, and baseline LDL-C.

Simvastatin

In two large, placebo-controlled clinical trials, the Scandinavian Simvastatin Survival Study (N=4,444 patients) and the Heart Protection Study (N=20,536 patients), the effects of treatment with simvastatin were assessed in patients at high risk of coronary events because of existing coronary heart disease, diabetes, peripheral vessel disease, history of stroke or other cerebrovascular disease. Simvastatin was proven to reduce: the risk of total mortality by reducing CHD deaths; the risk of non-fatal myocardial infarction and stroke; and the need for coronary and non-coronary revascularization procedures.

No incremental benefit of VYTORIN on cardiovascular morbidity and mortality over and above that demonstrated for simvastatin has been established.

14.2 Homozygous Familial Hypercholesterolemia (HoFH)

A double-blind, randomized, 12-week study was performed in patients with a clinical and/or genotypic diagnosis of HoFH. Data were analyzed from a subgroup of patients (n=14) receiving simvastatin 40 mg at baseline. Increasing the dose of simvastatin from 40 to 80 mg (n=5) produced a reduction of LDL-C of 13% from baseline on simvastatin 40 mg. Coadministered ezetimibe and simvastatin equivalent to VYTORIN (10/40 and 10/80 pooled, n=9), produced a reduction of LDL-C of 23% from baseline on simvastatin 40 mg. In those patients coadministered ezetimibe and simvastatin equivalent to VYTORIN (10/80, n=5), a reduction of LDL-C of 29% from baseline on simvastatin 40 mg was produced.

14.3 Chronic Kidney Disease (CKD)

The Study of Heart and Renal Protection (SHARP) was a multinational, randomized, placebo-controlled, double-blind trial that investigated the effect of VYTORIN on the time to a first major vascular event (MVE) among 9438 patients with moderate to severe chronic kidney disease (approximately one-third on dialysis at baseline) who did not have a history of myocardial infarction or coronary revascularization. An MVE was defined as nonfatal MI, cardiac death, stroke, or any revascularization procedure. Patients were allocated to treatment using a method that took into account the distribution of 8 important baseline characteristics of patients already enrolled and minimized the imbalance of those characteristics across the groups.

For the first year, 9438 patients were allocated 4:4:1, to VYTORIN 10/20, placebo, or simvastatin 20 mg daily, respectively. The 1-year simvastatin arm enabled the comparison of VYTORIN to simvastatin with regard to safety and effect on lipid levels. At 1 year the simvastatin-only arm was re-allocated 1:1 to VYTORIN 10/20 or placebo. A total of 9270 patients were ever allocated to VYTORIN 10/20 (n=4650) or placebo (n=4620) during the trial. The median follow-up duration was 4.9 years. Patients had a mean age of 61 years; 63% were male, 72% were Caucasian, and 23% were diabetic; and, for those not on dialysis at baseline, the median serum creatinine was 2.5 mg/dL and the median estimated glomerular filtration rate (eGFR) was 25.6 mL/min/1.73 m^2, with 94% of patients having an eGFR < 45 mL/min/1.73m^2. Eligibility did not depend on lipid levels. Mean LDL-C at baseline was 108 mg/dL. At 1 year, the mean LDL-C was 26% lower in the simvastatin arm and 38% lower in the VYTORIN arm relative to placebo. At the midpoint of the study (2.5 years), the mean LDL-C was 32% lower for VYTORIN relative to placebo. Patients no longer taking study medication were included in all lipid measurements.

In the primary intent-to-treat analysis, 639 (15.2%) of 4193 patients initially allocated to VYTORIN and 749 (17.9%) of 4191 patients initially allocated to placebo experienced an MVE. This corresponded to a relative risk reduction of 16% (p=0.001) (see Figure 1). Similarly, 526 (11.3%) of 4650 patients ever allocated to VYTORIN and 619 (13.4%) of 4620 patients ever allocated to placebo experienced a major atherosclerotic event (MAE; a subset of the MVE composite that excluded non-coronary cardiac deaths and hemorrhagic stroke), corresponding to a relative risk reduction of 17% (p=0.002). The trial demonstrated that treatment with VYTORIN 10/20 mg versus placebo reduced the risk for MVE and MAE in this CKD population. The study design precluded drawing conclusions regarding the independent contribution of either ezetimibe or simvastatin to the observed effect.

The treatment effect of VYTORIN on MVE was attenuated among patients on dialysis at baseline compared with those not on dialysis at baseline. Among 3023 patients on dialysis at baseline, VYTORIN reduced the risk of MVE by 6% (RR 0.94: 95% CI 0.80-1.09) compared with 22% (RR 0.78: 95% CI 0.69-0.89) among 6247 patients not on dialysis at baseline (interaction P=0.08).

Figure 1: Effect of VYTORIN on the Primary Endpoint of Risk of Major Vascular Events

The individual components of MVE in all patients ever allocated to VYTORIN or placebo are presented in Table 12.

Table 12 Number of First Events for Each Component of the Major Vascular Event Composite Endpoint in SHARP [Intention-to-treat analysis on all SHARP patients ever allocated to VYTORIN or placebo]
Outcome | VYTORIN 10/20 (N=4650) | Placebo (N=4620) | Risk Ratio (95% CI) | P-value
Major Vascular Events | 701 (15.1%) | 814 (17.6%) | 0.85 (0.77-0.94) | 0.001
Nonfatal MI | 134 (2.9%) | 159 (3.4%) | 0.84 (0.66-1.05) | 0.12
Cardiac Death | 253 (5.4%) | 272 (5.9%) | 0.93 (0.78-1.10) | 0.38
Any Stroke | 171 (3.7%) | 210 (4.5%) | 0.81 (0.66-0.99) | 0.038
Non-hemorrhagic Stroke | 131 (2.8%) | 174 (3.8%) | 0.75 (0.60-0.94) | 0.011
Hemorrhagic Stroke | 45 (1.0%) | 37 (0.8%) | 1.21 (0.78-1.86) | 0.40
Any Revascularization | 284 (6.1%) | 352 (7.6%) | 0.79 (0.68-0.93) | 0.004

Among patients not on dialysis at baseline, VYTORIN did not reduce the risk of progressing to end-stage renal disease compared with placebo (RR 0.97: 95% CI 0.89-1.05).

16 HOW SUPPLIED/STORAGE AND HANDLING

No. 3873 — Tablets VYTORIN 10/10 are white to off-white capsule-shaped tablets with code "311" on one side.

They are supplied as follows:

Bottles of 30 | NDC 54868-5250-0

No. 3874 — Tablets VYTORIN 10/20 are white to off-white capsule-shaped tablets with code "312" on one side.

They are supplied as follows:

Bottles of 15 | NDC 54868-5187-2
Bottles of 30 | NDC 54868-5187-0

No. 3875 — Tablets VYTORIN 10/40 are white to off-white capsule-shaped tablets with code "313" on one side.

They are supplied as follows:

Bottles of 30 | NDC 54868-5189-0
Bottles of 90 | NDC 54868-5189-1

No. 3876 — Tablets VYTORIN 10/80 are white to off-white capsule-shaped tablets with code "315" on one side.

They are supplied as follows:

Bottles of 30 | NDC 54868-5259-0
Bottles of 90 | NDC 54868-5259-1

Storage

Store at 20-25°C (68-77°F). [See USP Controlled Room Temperature.] Keep container tightly closed.

17 PATIENT COUNSELING INFORMATION

See FDA-Approved Patient Labeling (Patient Information).

Patients should be advised to adhere to their National Cholesterol Education Program (NCEP)-recommended diet, a regular exercise program, and periodic testing of a fasting lipid panel.

Patients should be advised about substances they should not take concomitantly with VYTORIN [see Contraindications (4) and Warnings and Precautions (5.1)]. Patients should also be advised to inform other healthcare professionals prescribing a new medication or increasing the dose of an existing medication that they are taking VYTORIN.

17.1 Muscle Pain

All patients starting therapy with VYTORIN should be advised of the risk of myopathy, including rhabdomyolysis, and told to report promptly any unexplained muscle pain, tenderness or weakness. Patients using the 10/80-mg dose should be informed that the risk of myopathy, including rhabdomyolysis, is increased with the use of the 10/80-mg dose. The risk of myopathy, including rhabdomyolysis, occurring with use of VYTORIN is increased when taking certain types of medication or consuming larger quantities of grapefruit juice. Patients should discuss all medication, both prescription and over the counter, with their healthcare professional.

17.2 Liver Enzymes

It is recommended that liver function tests be performed before the initiation of VYTORIN, and thereafter when clinically indicated. All patients treated with VYTORIN should be advised to report promptly any symptoms that may indicate liver injury, including fatigue, anorexia, right upper abdominal discomfort, dark urine or jaundice.

17.3 Pregnancy

Women of childbearing age should be advised to use an effective method of birth control to prevent pregnancy while using VYTORIN. Discuss future pregnancy plans with your patients, and discuss when to stop taking VYTORIN if they are trying to conceive. Patients should be advised that if they become pregnant they should stop taking VYTORIN and call their healthcare professional.

17.4 Breast-feeding

Women who are breast-feeding should be advised to not use VYTORIN. Patients who have a lipid disorder and are breast-feeding should be advised to discuss the options with their healthcare professional.

Manufactured for: MSP Distribution Services (C) LLC, a subsidiary of
MERCK & CO., INC., Whitehouse Station, NJ 08889, USA

By:
MSD International GmbH (Singapore Branch)
Singapore 637766

Or

Merck Sharp & Dohme (Italia) S.p.A.
Via Emilia, 21
27100 – Pavia, Italy

Or

Merck Sharp & Dohme Ltd.
Cramlington, Northumberland, UK NE23 3JU

Or

Jointly manufactured by:
Merck Sharp & Dohme (Italia) S.p.A.
Via Emilia, 21
27100 – Pavia, Italy
and
MSD International GmbH (Singapore Branch)
Singapore 637766

U.S. Patent Nos. 5,846,966 and RE42,461

Revised: 02/2012

9619523

Distributed and Repackaged by:
Physicians Total Care, Inc.
Tulsa, Oklahoma 74146

PATIENT INFORMATION

VYTORIN® (ezetimibe/simvastatin) Tablets
Patient Information about VYTORIN (VI-tor-in)
Generic name: ezetimibe/simvastatin tablets

Read this information carefully before you start taking VYTORIN®. Review this information each time you refill your prescription for VYTORIN as there may be new information. This information does not take the place of talking with your doctor about your medical condition or your treatment. If you have any questions about VYTORIN, ask your doctor. Only your doctor can determine if VYTORIN is right for you.

What is VYTORIN?

VYTORIN contains two cholesterol-lowering medications, ezetimibe and simvastatin. VYTORIN is a prescription medicine used to lower levels of total cholesterol, LDL (bad) cholesterol, and fatty substances called triglycerides in the blood. In addition, VYTORIN raises levels of HDL (good) cholesterol. VYTORIN is for patients who cannot control their cholesterol levels by diet and exercise alone. You should stay on a cholesterol-lowering diet while taking this medicine.

VYTORIN works to reduce your cholesterol in two ways. It reduces the cholesterol absorbed in your digestive tract, as well as the cholesterol your body makes by itself. VYTORIN does not help you lose weight.

VYTORIN has not been shown to reduce heart attacks or strokes more than simvastatin alone.

The usual dose of VYTORIN is 10/10 mg to 10/40 mg 1 time each day.

VYTORIN 10/80 mg increases your chance of developing muscle damage. The 10/80 mg dose should only be used by people who:

- have been taking VYTORIN 10/80 mg chronically (such as 12 months or more) without having muscle damage
- do not need to take certain other medicines with VYTORIN that would increase your chance of getting muscle damage.

If you are unable to reach your LDL-cholesterol goal using VYTORIN 10/40 mg, your doctor should switch you to another cholesterol-lowering medicine.

For more information about cholesterol, see the section called "What should I know about high cholesterol?"

Who should not take VYTORIN?

Do not take VYTORIN if you take:

- Certain anti-fungal medicines including:
  - itraconazole
  - ketoconazole
  - posaconazole
- HIV protease inhibitors (indinavir, nelfinavir, ritonavir, saquinavir, tipranavir, or atazanavir)
- Certain hepatitis C virus protease inhibitors (such as boceprevir or telaprevir)
- Certain antibiotics, including:
  - erythromycin
  - clarithromycin
  - telithromycin
- nefazodone
- A fibric acid medicine for lowering cholesterol called gemfibrozil
- cyclosporine
- danazol

Ask your doctor if you are not sure if your medicine is listed above.

Also do not take VYTORIN:

- If you are allergic to ezetimibe or simvastatin, the active ingredients in VYTORIN, or to the inactive ingredients. For a list of inactive ingredients, see the "Inactive ingredients" section at the end of this information sheet.
- If you have active liver disease or repeated blood tests indicating possible liver problems.
- If you are pregnant, or think you may be pregnant, or planning to become pregnant or breast-feeding.
- If you are a woman of childbearing age, you should use an effective method of birth control to prevent pregnancy while using VYTORIN.

VYTORIN has not been studied in children under 10 years of age.

What should I tell my doctor before and while taking VYTORIN?

Tell your doctor right away if you have unexplained muscle pain, tenderness, or weakness while you take VYTORIN. Muscle problems, including muscle breakdown, can be serious in some people and rarely cause kidney damage that can lead to death.

The risk of muscle breakdown is greater at higher doses of VYTORIN, particularly the 10/80 mg dose.

The risk of muscle breakdown is greater in people 65 years of age and older, females, and people with kidney or thyroid problems.

Taking VYTORIN with certain substances can increase the risk of muscle problems. It is especially important to tell your doctor if you take:

- fibric acid derivatives (such as fenofibrate)
- amiodarone (a drug used to treat an irregular heartbeat)
- verapamil, diltiazem, amlodipine, or ranolazine (drugs used to treat high blood pressure, chest pain associated with heart disease, or other heart conditions)
- large quantities of grapefruit juice (more than 1 quart daily)
- colchicine (a medicine used to treat gout)
- voriconazole (an anti-fungal medicine)
- large doses of niacin or nicotinic acid

Tell your doctor if you are taking niacin or a niacin-containing product, as this may increase your risk of muscle problems, especially if you are Chinese.

It is also important to tell your doctor if you are taking coumarin anticoagulants (drugs that prevent blood clots, such as warfarin).

Tell your doctor about all the medicines you take, including any prescription and nonprescription medicines, vitamins, and herbal supplements.

If you have more than 1 doctor, tell all of your doctors that you take VYTORIN. This is especially important when they prescribe a new medicine or increase the dose of your other medicines.

Tell your doctor about all your medical conditions including allergies.

Tell your doctor if you:

- drink substantial quantities of alcohol or ever had liver problems. VYTORIN may not be right for you.
- are pregnant or plan to become pregnant. Do not use VYTORIN if you are pregnant, trying to become pregnant or suspect that you are pregnant. If you become pregnant while taking VYTORIN, stop taking it and contact your doctor immediately.
- are breast-feeding. Do not use VYTORIN if you are breast-feeding.

Tell other doctors prescribing a new medication that you are taking VYTORIN.

How should I take VYTORIN?

- Take VYTORIN exactly as your doctor tells you to take it.
- Take VYTORIN once a day, in the evening, with or without food.
- If you miss a dose, do not take an extra dose. Just resume your usual schedule.
- Continue to follow a cholesterol-lowering diet while taking VYTORIN. Ask your doctor if you need diet information.
- Keep taking VYTORIN unless your doctor tells you to stop. If you stop taking VYTORIN, your cholesterol may rise again.

What should I do in case of an overdose?

Contact your doctor immediately.

What are the possible side effects of VYTORIN?

See your doctor regularly to check your cholesterol level and to check for side effects. Your doctor should do blood tests to check your liver before you start taking VYTORIN and if you have any symptoms of liver problems while you take VYTORIN. Call your doctor right away if you have the following symptoms of liver problems:

- feel tired or weak
- loss of appetite
- upper belly pain
- dark urine
- yellowing of your skin or the whites of your eyes

In clinical studies patients reported the following common side effects while taking VYTORIN: headache, muscle pain, and diarrhea (see What should I tell my doctor before and while taking VYTORIN?).

The following side effects have been reported in general use with VYTORIN or with ezetimibe or simvastatin tablets (tablets that contain the active ingredients of VYTORIN):

- allergic reactions including swelling of the face, lips, tongue, and/or throat that may cause difficulty in breathing or swallowing (which may require treatment right away), rash, hives; raised red rash, sometimes with target-shaped lesions; joint pain; muscle pain; alterations in some laboratory blood tests; liver problems (sometimes serious); inflammation of the pancreas; nausea; dizziness; tingling sensation; depression; gallstones; inflammation of the gallbladder; trouble sleeping; poor memory; memory loss; confusion; erectile dysfunction; breathing problems including persistent cough and/or shortness of breath or fever.

Tell your doctor if you are having these or any other medical problems while on VYTORIN. This is not a complete list of side effects. For a complete list, ask your doctor or pharmacist.

What should I know about high cholesterol?

Cholesterol is a type of fat found in your blood. Cholesterol comes from two sources. It is produced by your body and it comes from the food you eat. Your total cholesterol is made up of both LDL and HDL cholesterol.

LDL cholesterol is called "bad" cholesterol because it can build up in the wall of your arteries and form plaque. Over time, plaque build-up can cause a narrowing of the arteries. This narrowing can slow or block blood flow to your heart, brain, and other organs. High LDL cholesterol is a major cause of heart disease and one of the causes for stroke.

HDL cholesterol is called "good" cholesterol because it keeps the bad cholesterol from building up in the arteries.

Triglycerides also are fats found in your body.

General Information about VYTORIN

Medicines are sometimes prescribed for conditions that are not mentioned in patient information leaflets. Do not use VYTORIN for a condition for which it was not prescribed. Do not give VYTORIN to other people, even if they have the same condition you have. It may harm them.

This summarizes the most important information about VYTORIN. If you would like more information, talk with your doctor. You can ask your pharmacist or doctor for information about VYTORIN that is written for health professionals. For additional information, visit the following web site: vytorin.com.

Inactive ingredients:

Butylated hydroxyanisole NF, citric acid monohydrate USP, croscarmellose sodium NF, hypromellose USP, lactose monohydrate NF, magnesium stearate NF, microcrystalline cellulose NF, and propyl gallate NF.

Manufactured for: MSP Distribution Services (C) LLC, a subsidiary of
MERCK & CO., INC., Whitehouse Station, NJ 08889, USA

This patient information has been approved by the U.S. Food and Drug Administration

Revised: 02/2012

9619523

PRINCIPAL DISPLAY PANEL - Bottle Label 10/10

VYTORIN® 10/10
(ezetimibe/simvastatin)

Each tablet contains 10 mg ezetimibe and
10 mg simvastatin.

Store at 20-25°C (68-77°F).
[See USP Controlled Room Temperature.]
Keep container tightly closed.

Rx only

USUAL ADULT DOSAGE:
See accompanying circular.

PRINCIPAL DISPLAY PANEL - Bottle Label 10/20

VYTORIN® 10/20
(ezetimibe/simvastatin)

Each tablet contains 10 mg ezetimibe and
20 mg simvastatin.

Store at 20-25°C (68-77°F).
[See USP Controlled Room Temperature.]
Keep container tightly closed.

Rx only

USUAL ADULT DOSAGE:
See accompanying circular.

PRINCIPAL DISPLAY PANEL - Bottle Label 10/40

VYTORIN® 10/40
(ezetimibe/simvastatin)

Each tablet contains 10 mg ezetimibe and
40 mg simvastatin.

Store at 20-25°C (68-77°F).
[See USP Controlled Room Temperature.]
Keep container tightly closed.

Rx only

USUAL ADULT DOSAGE:
See accompanying circular.

PRINCIPAL DISPLAY PANEL - Bottle Label 10/80

VYTORIN® 10/80
(ezetimibe/simvastatin)

Each tablet contains 10 mg ezetimibe and
80 mg simvastatin.

Store at 20-25°C (68-77°F).
[See USP Controlled Room Temperature.]
Keep container tightly closed.

Rx only

USUAL ADULT DOSAGE:
See accompanying circular.